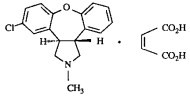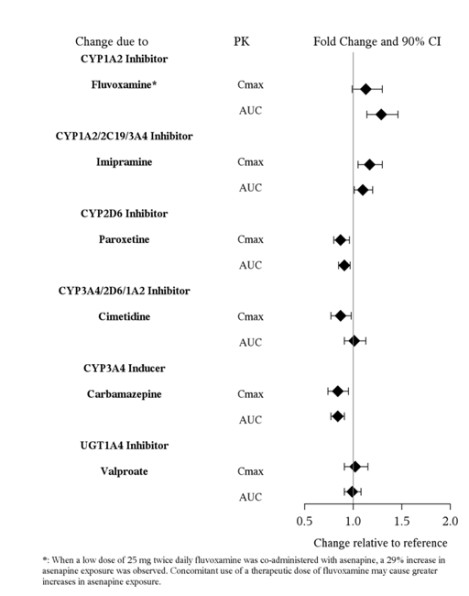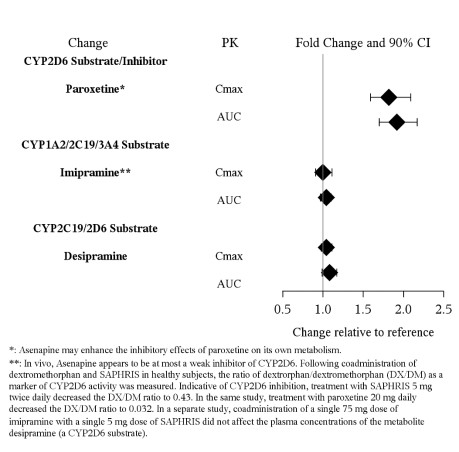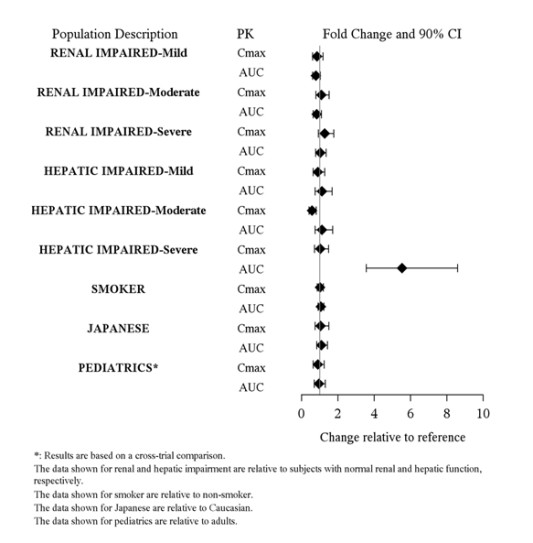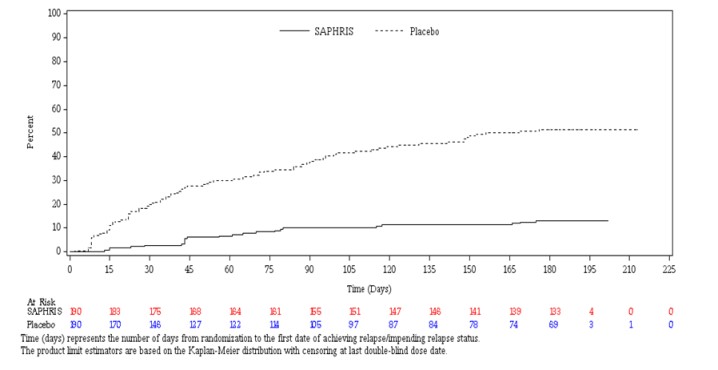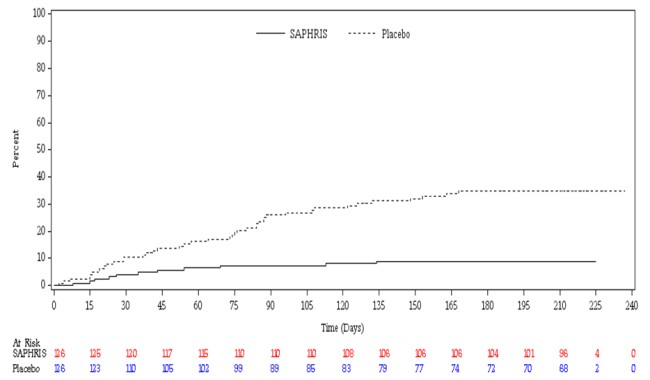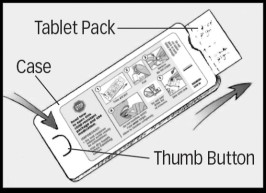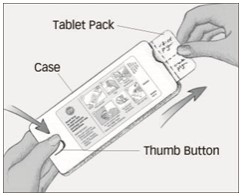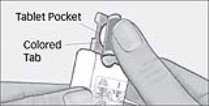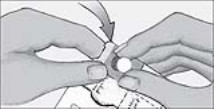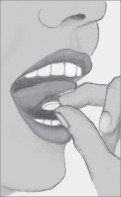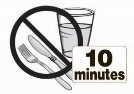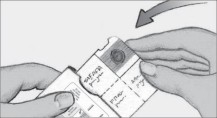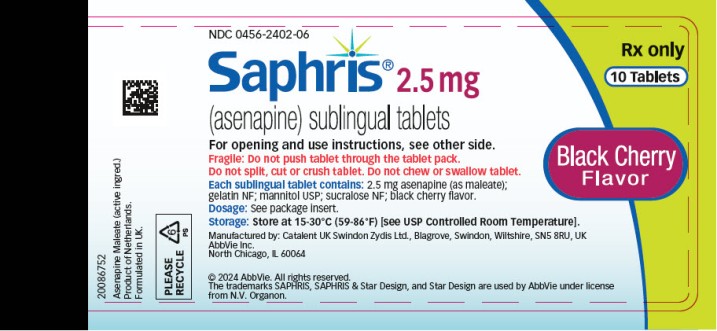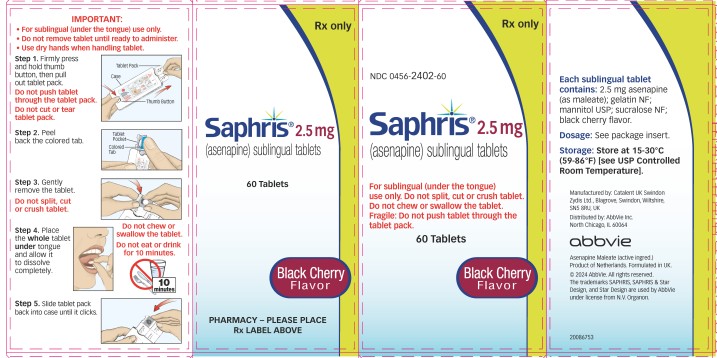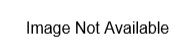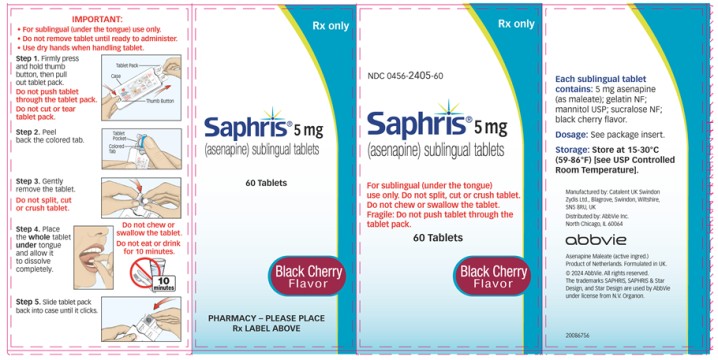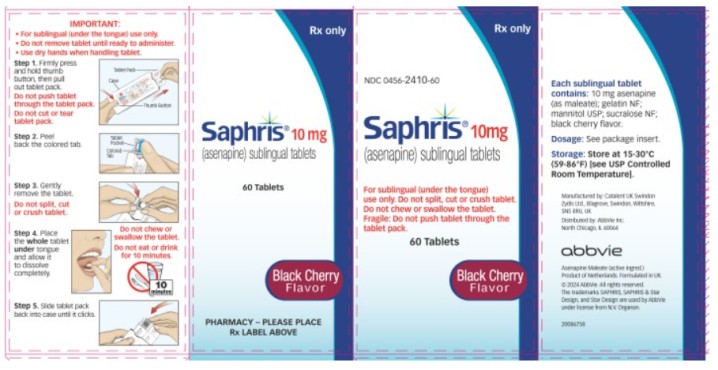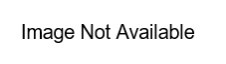 DRUG LABEL: SAPHRIS
NDC: 0456-2402 | Form: TABLET
Manufacturer: Allergan, Inc.
Category: prescription | Type: HUMAN PRESCRIPTION DRUG LABEL
Date: 20250131

ACTIVE INGREDIENTS: ASENAPINE MALEATE 2.5 mg/1 1
INACTIVE INGREDIENTS: GELATIN, UNSPECIFIED; MANNITOL; SUCRALOSE

HIGHLIGHTS OF PRESCRIBING INFORMATION

These highlights do not include all the information needed to use SAPHRIS (asenapine) sublingual tablets safely and effectively. See full prescribing information for SAPHRIS.
SAPHRIS® (asenapine) sublingual tablets
Initial U.S. Approval: 2009

RECENT MAJOR CHANGES

Warnings and Precautions (5.11) 01/2025

WARNING: INCREASED MORTALITY IN ELDERLY PATIENTS WITH DEMENTIA-RELATED PSYCHOSIS

See full prescribing information for complete boxed warning.

Elderly patients with dementia-related psychosis treated with antipsychotic drugs are at an increased risk of death. SAPHRIS is not approved for the treatment of patients with dementia-related psychosis. (5.1, 5.2)

1 INDICATIONS AND USAGE

SAPHRIS is an atypical antipsychotic indicated for (1):

- Schizophrenia in adults
- Bipolar I disorder
  ○ Acute monotherapy treatment of manic or mixed episodes, in adults and pediatric patients 10 to 17 years of age
  ○ Adjunctive treatment to lithium or valproate in adults
  ○ Maintenance monotherapy treatment in adults

2 DOSAGE AND ADMINISTRATION

 | Starting Dose | Recommended Dose | Maximum Dose
Schizophrenia – acute treatment in adults (2.2) | 5 mg sublingually twice daily | 5 mg sublingually twice daily | 10 mg sublingually twice daily
Schizophrenia – maintenance treatment in adults (2.2) | 5 mg sublingually twice daily | 5-10 mg sublingually twice daily | 10 mg sublingually twice daily
Bipolar mania – adults: acute and maintenance monotherapy (2.3) | 5-10 mg sublingually twice daily | 5-10 mg sublingually twice daily | 10 mg sublingually twice daily
Bipolar mania –pediatric patients (10 to 17 years): monotherapy (2.3) | 2.5 mg sublingually twice daily | 2.5-10 mg sublingually twice daily | 10 mg sublingually twice daily
Bipolar mania – adults: as an adjunct to lithium or valproate (2.3) | 5 mg sublingually twice daily | 5-10 mg sublingually twice daily | 10 mg sublingually twice daily

- Do not swallow tablet. SAPHRIS sublingual tablets should be placed under the tongue and left to dissolve completely. The tablet will dissolve in saliva within seconds. Eating and drinking should be avoided for 10 minutes after administration. (2.1, 17)

3 DOSAGE FORMS AND STRENGTHS

Sublingual tablets, black cherry flavor: 2.5 mg, 5 mg and 10 mg (3)

4 CONTRAINDICATIONS

- Severe hepatic impairment (Child-Pugh C). (8.7, 12.3)
- Known hypersensitivity to SAPHRIS (asenapine), or to any components in the formulation. (4, 5.6, 17)

5 WARNINGS AND PRECAUTIONS

- Cerebrovascular Adverse Reactions in Elderly Patients with Dementia-Related Psychosis: Increased incidence of cerebrovascular adverse reactions (e.g., stroke, transient ischemic attack). (5.2)
- Neuroleptic Malignant Syndrome: Manage with immediate discontinuation and close monitoring. (5.3)
- Tardive Dyskinesia: Discontinue if clinically appropriate. (5.4)
- Metabolic Changes: Monitor for hyperglycemia/diabetes mellitus, dyslipidemia, and weight gain. (5.5)
- Orthostatic Hypotension: Monitor heart rate and blood pressure and warn patients with known cardiovascular or cerebrovascular disease, and risk of dehydration or syncope. (5.7)
- Leukopenia, Neutropenia, and Agranulocytosis: Perform complete blood counts (CBC) in patients with pre-existing low white blood cell count (WBC) or history of leukopenia or neutropenia. Consider discontinuing SAPHRIS if a clinically significant decline in WBC occurs in absence of other causative factors. (5.9)
- QT Prolongation: Increases in QT interval; avoid use with drugs that also increase the QT interval and in patients with risk factors for prolonged QT interval. (5.10)
- Seizures: Use cautiously in patients with a history of seizures or with conditions that lower the seizure threshold. (5.12)
- Potential for Cognitive and Motor Impairment: Use caution when operating machinery. (5.13)

6 ADVERSE REACTIONS

The most commonly observed adverse reactions (incidence ≥5% and at least twice that for placebo) were (6.1):

- Schizophrenia Adults: akathisia, oral hypoesthesia, somnolence.
- Bipolar I Disorder Adults (Monotherapy): somnolence, oral hypoesthesia, dizziness, extrapyramidal symptoms (excluding akathisia) and akathisia.
- Bipolar I Disorder Pediatric Patients (Monotherapy): somnolence, dizziness, dysgeusia, oral paresthesia, nausea, increased appetite, fatigue, increased weight.
- Bipolar I Disorder Adults (Adjunctive): somnolence, oral hypoesthesia.

To report SUSPECTED ADVERSE REACTIONS, contact AbbVie, Inc. at 1-800-678-1605 or FDA at 1-800-FDA-1088 or www.fda.gov/medwatch.

7 DRUG INTERACTIONS

- Antihypertensive Drugs: SAPHRIS may cause hypotension. (5.7, 7.1, 12.3)
- Paroxetine (CYP2D6 substrate and inhibitor): Reduce paroxetine by half when used in combination with SAPHRIS. (7.1, 12.3)

8 USE IN SPECIFIC POPULATIONS

- Pregnancy: May cause extrapyramidal and/or withdrawal symptoms in neonates with third trimester exposure. (8.1)
- Pediatric Use: Safety and efficacy in the treatment of bipolar I disorder in patients less than 10 years of age, and patients with schizophrenia ages less than 12 years have not been evaluated. (8.4)

FULL PRESCRIBING INFORMATION

WARNING: INCREASED MORTALITY IN ELDERLY PATIENTS WITH DEMENTIA-RELATED PSYCHOSIS

Elderly patients with dementia-related psychosis treated with antipsychotic drugs are at an increased risk of death. SAPHRIS® (asenapine) is not approved for the treatment of patients with dementia-related psychosis [see Warnings and Precautions (5.1, 5.2)].

1 INDICATIONS AND USAGE

SAPHRIS is indicated for:

- Schizophrenia in adults [see Clinical Studies (14.1)]
- Bipolar I disorder [see Clinical Studies (14.2)]
  • Acute monotherapy of manic or mixed episodes, in adults and pediatric patients 10 to 17 years of age
  • Adjunctive treatment to lithium or valproate in adults
  • Maintenance monotherapy treatment in adults

2 DOSAGE AND ADMINISTRATION

2.1 Administration Instructions

SAPHRIS is a sublingual tablet. To ensure optimal absorption, patients should be instructed to place the tablet under the tongue and allow it to dissolve completely. The tablet will dissolve in saliva within seconds. SAPHRIS sublingual tablets should not be split, crushed, chewed, or swallowed [see Clinical Pharmacology (12.3)]. Patients should be instructed to not eat or drink for 10 minutes after administration [see Clinical Pharmacology (12.3)].

2.2 Schizophrenia

The recommended dose of SAPHRIS is 5 mg given twice daily. In short-term controlled trials, there was no suggestion of added benefit with a 10 mg twice daily dose, but there was a clear increase in certain adverse reactions. If tolerated, daily dosage can be increased to 10 mg twice daily after one week. The safety of doses above 10 mg twice daily has not been evaluated in clinical studies [see Clinical Studies (14.1)].

2.3 Bipolar I Disorder

Acute Treatment of Manic or Mixed Episodes:

Monotherapy in Adults: The recommended starting and treatment dose of SAPHRIS is 5 mg to 10 mg twice daily. The safety of doses above 10 mg twice daily has not been evaluated in clinical trials [see Clinical Studies (14.2)].

Monotherapy in Pediatric Patients: The recommended dose of SAPHRIS is 2.5 mg to 10 mg twice daily in pediatric patients 10 to 17 years of age, and dose may be adjusted for individual response and tolerability. The starting dose of SAPHRIS is 2.5 mg twice daily. After 3 days, the dose can be increased to 5 mg twice daily, and from 5 mg to 10 mg twice daily after 3 additional days. Pediatric patients aged 10 to 17 years appear to be more sensitive to dystonia with initial dosing with SAPHRIS when the recommended escalation schedule is not followed [see Use in Specific Populations (8.4)]. The safety of doses greater than 10 mg twice daily has not been evaluated in clinical trials [see Use in Specific Populations (8.4) and Clinical Pharmacology (12.3)].

Adjunctive Therapy in Adults: The recommended starting dose of SAPHRIS is 5 mg twice daily when administered as adjunctive therapy with either lithium or valproate. Depending on the clinical response and tolerability in the individual patient, the dose can be increased to 10 mg twice daily. The safety of doses above 10 mg twice daily as adjunctive therapy with lithium or valproate has not been evaluated in clinical trials.

For patients on SAPHRIS, whether used as monotherapy or as adjunctive therapy with lithium or valproate, it is generally recommended that responding patients continue treatment beyond the acute episode.

Maintenance Treatment of Bipolar I Disorder:

Monotherapy in Adults: Continue on the SAPHRIS dose that the patient received during stabilization (5 mg to 10 mg twice daily). Depending on the clinical response and tolerability in the individual patient, a dose of 10 mg twice daily can be decreased to 5 mg twice daily. The safety of doses above 10 mg twice daily has not been evaluated in clinical trials [see Clinical Studies (14.2)].

3 DOSAGE FORMS AND STRENGTHS

- SAPHRIS 2.5 mg tablets, black cherry flavor, are round, white to off-white sublingual tablets, with a hexagon on one side.
- SAPHRIS 5 mg tablets, black cherry flavor, are round, white to off-white sublingual tablets, with “5” on one side within a circle.
- SAPHRIS 10 mg tablets, black cherry flavor, are round, white to off-white sublingual tablets, with “10” on one side within a circle.

4 CONTRAINDICATIONS

SAPHRIS is contraindicated in patients with:

- Severe hepatic impairment (Child-Pugh C) [see Specific Populations (8.7), Clinical Pharmacology (12.3)].
- A history of hypersensitivity reactions to asenapine. Reactions have included anaphylaxis, angioedema, hypotension, tachycardia, swollen tongue, dyspnea, wheezing and rash [see Warnings and Precautions (5.6), Adverse Reactions (6)].

5 WARNINGS AND PRECAUTIONS

5.1 Increased Mortality in Elderly Patients with Dementia-Related Psychosis

Elderly patients with dementia-related psychosis treated with antipsychotic drugs are at an increased risk of death. Analyses of 17 placebo-controlled trials (modal duration of 10 weeks), largely in patients taking atypical antipsychotic drugs, revealed a risk of death in drug-treated patients of between 1.6 to 1.7 times the risk of death in placebo-treated patients. Over the course of a typical 10-week controlled trial, the rate of death in drug-treated patients was about 4.5%, compared to a rate of about 2.6% in the placebo group.

Although the causes of death were varied, most of the deaths appeared to be either cardiovascular (e.g., heart failure, sudden death) or infectious (e.g., pneumonia) in nature. SAPHRIS is not approved for the treatment of patients with dementia-related psychosis [see Boxed Warning and Warnings and Precautions (5.2)].

5.2 Cerebrovascular Adverse Events, Including Stroke, In Elderly Patients with Dementia-Related Psychosis

In placebo-controlled trials in elderly subjects with dementia, patients randomized to risperidone, aripiprazole, and olanzapine had a higher incidence of stroke and transient ischemic attack, including fatal stroke. SAPHRIS is not approved for the treatment of patients with dementia-related psychosis [see Boxed Warning, Warnings and Precautions (5.1)].

5.3 Neuroleptic Malignant Syndrome

A potentially fatal symptom complex sometimes referred to as Neuroleptic Malignant Syndrome (NMS) has been reported in association with administration of antipsychotic drugs. Clinical manifestations of NMS are hyperpyrexia, muscle rigidity, delirium, and autonomic instability. Additional signs may include elevated creatine phosphokinase, myoglobinuria (rhabdomyolysis), and acute renal failure. If NMS is suspected, immediately discontinue SAPHRIS and provide intensive symptomatic treatment and monitoring.

5.4 Tardive Dyskinesia

Tardive dyskinesia, a syndrome consisting of potentially irreversible, involuntary, dyskinetic movements, may develop in patients treated with antipsychotic drugs, including SAPHRIS. The risk appears to be highest among the elderly, especially elderly women, but it is not possible to predict which patients are likely to develop the syndrome. Whether antipsychotic drug products differ in their potential to cause tardive dyskinesia is unknown.

The risk of tardive dyskinesia and the likelihood that it will become irreversible increase with the duration of treatment and the cumulative dose. The syndrome can develop after a relatively brief treatment period, even at low doses. It may also occur after discontinuation of treatment.

There is no known treatment for tardive dyskinesia, although the syndrome may remit, partially or completely, if antipsychotic treatment is discontinued. Antipsychotic treatment itself, however, may suppress (or partially suppress) the signs and symptoms of the syndrome, possibly masking the underlying process. The effect that symptomatic suppression has upon the long-term course of tardive dyskinesia is unknown.

Given these considerations, SAPHRIS should be prescribed in a manner most likely to reduce the risk of tardive dyskinesia. Chronic antipsychotic treatment should generally be reserved for patients: 1) who suffer from a chronic illness that is known to respond to antipsychotic drugs; and 2) for whom alternative, effective, but potentially less harmful treatments are not available or appropriate. In patients who do require chronic treatment, use the lowest dose and the shortest duration of treatment producing a satisfactory clinical response should be sought. Periodically reassess the need for continued treatment.

If signs and symptoms of TD appear in a patient on SAPHRIS, drug discontinuation should be considered. However, some patients may require treatment with SAPHRIS despite the presence of the syndrome.

5.5 Metabolic Changes

Atypical antipsychotic drugs, including SAPHRIS, have caused metabolic changes, including hyperglycemia, diabetes mellitus, dyslipidemia, and body weight gain. Although all of the drugs in the class to date have been shown to produce some metabolic changes, each drug has its own specific risk profile.

Hyperglycemia and Diabetes Mellitus

Hyperglycemia, in some cases extreme and associated with ketoacidosis or hyperosmolar coma or death, has been reported in patients treated with atypical antipsychotics. There have been reports of hyperglycemia in patients treated with SAPHRIS. Assess fasting plasma glucose before or soon after initiation of antipsychotic medication, and monitor periodically during long-term treatment.

Adult Patients: Pooled data from the short-term placebo-controlled schizophrenia and bipolar mania trials are presented in Table 1.

TABLE 1: Changes in Fasting Glucose in Adult Patients
 | Schizophrenia (6-weeks) |  |  |  |  | Bipolar I Disorder (3-weeks)
 | Placebo | SAPHRIS |  |  |  | Placebo | SAPHRIS
 |  | 5 mg twice daily |  | 10 mg twice daily | 5 or 10 mg twice daily§ |  | 5 mg twice daily | 10 mg twice daily | 5 or 10 mg twice daily†
Mean Change from Baseline in Fasting Glucose at Endpoint
Change from Baseline (mg/dL) (N*) | -0.2 (232) |  | 3.8 (158) | 1.1 (153) | 3.2 (377) | 0 (174) | 4.1 (84) | 3.5 (81) | 1.7 (321)
Proportion of Patients with Shifts from Baseline to Endpoint
Normal to High <100 to ≥126 mg/dL | 4.1% |  | 4.5% | 4.5% | 5.0% | 2.4% | 0% | 1.7% | 1.8%
(n/N**) | (7/170) |  | (5/111) | (5/111) | (13/262) | (3/126) | (0/53) | (1/60) | (4/224)
Borderline to High ≥100 and <126 to ≥126 mg/dL | 5.9% |  | 6.8% | 6.3% | 10.5% | 0% | 12.5% | 15.8% | 12.8%
(n/N**) | (3/51) |  | (3/44) | (2/32) | (10/95) | (0/39) | (3/24) | (3/19) | (10/78)

N* = Number of patients who had assessments at both Baseline and Endpoint.

N** = Number of patients at risk at Baseline with assessments at both Baseline and Endpoint.

§ Includes patients treated with flexible dose of SAPHRIS 5 or 10 mg twice daily (N=90).

† Includes patients treated with flexible dose of SAPHRIS 5 or 10 mg twice daily (N=379).

In a 52-week, double-blind, comparator-controlled trial that included primarily patients with schizophrenia, the mean increase from baseline of fasting glucose was 2.4 mg/dL.

Pediatric Patients: Data from the short-term, placebo-controlled trial in pediatric patients with bipolar I disorder are shown in Table 2.

TABLE 2: Changes in Fasting Glucose in Pediatric Subjects
 | Bipolar I Disorder (3-weeks)
 | Placebo | SAPHRIS 2.5 mg twice daily | SAPHRIS 5 mg twice daily | SAPHRIS 10 mg twice daily
 | Mean Change from Baseline in Fasting Glucose at Endpoint
Change from Baseline (mg/dL) (N*) | -2.24 (56) | 1.43 (51) | -0.45 (57) | 0.34 (52)
 | Proportion of Subjects with Shifts from Baseline to Endpoint
Normal to High>45 & <100 to ≥126 mg/dL | 0% | 0% | 1.8% | 0%
(n/N*) | (0/56) | (0/51) | (1/57) | (0/52)

N* = Number of subjects who had assessments at both Baseline and Endpoint.

Dyslipidemia

Atypical antipsychotics cause adverse alterations in lipids. Before or soon after initiation of antipsychotic medication, obtain a fasting lipid profile at baseline and monitor periodically during treatment.

Adult Patients: Pooled data from the short-term, placebo-controlled schizophrenia and bipolar mania trials are presented in Table 3.

TABLE 3: Changes in Lipids in Adult Patients
 | Schizophrenia (6-weeks) |  |  |  |  |  |  | Bipolar I Disorder (3-weeks)
 | Placebo | SAPHRIS |  |  |  |  |  | Placebo |  | SAPHRIS
 |  | 5 mg twice daily |  | 10 mg twice daily |  | 5 or 10 mg twice daily§ |  |  |  | 5 mg twice daily | 10 mg twice daily | 5 or 10 mg twice daily†
Mean Change from Baseline (mg/dL)
Total cholesterol (N*) | -2.2 (351) |  | -2.4 (258) |  | 3.3 (199) |  | 0.4 (539) |  | -1.6 (278) | -1.6 (108) | -4.7 (95) | -0.5 (525)
LDL (N*) | 0.1 (285) |  | -0.2 (195) |  | 2.6 (195) |  | 1.3 (465) |  | 1.4(271) | -2.5 (101) | -4.1 (94) | -0.3(499)
HDL (N*) | 0.5 (290) |  | 0.4 (199) |  | 1.0 (199) |  | 0.5 (480) |  | 0.2 (278) | 0.1 (108) | 0.7 (95) | 0.7 (525)
Fasting triglycerides (N*) | -7.6 (233) |  | -1.9 (159) |  | 0.1 (154) |  | 3.8 (380) |  | -16.9(222) | 3.9 (89) | -8.5 (85) | -3.0(411)
Proportion of Patients with Shifts from Baseline to Endpoint
Total cholesterol Normal to High <200 to ≥240 (mg/dL) (n/N*) | 1.3% (3/225) |  | 0.6% (1/161) |  | 2.2% (3/134) |  | 1.7% (6/343) |  | 1.2% (2/174) | 3.0% (2/66) | 0 (0/63) | 2.1% (7/333)
LDL Normal to High <100 to ≥160 (mg/dL) (n/N*) | 1.7% (2/117) |  | 0.0% (0/80) |  | 1.2% (1/86) |  | 1.0% (2/196) |  | 1.9% (2/108) | 2.4% (1/41) | 0 (0/41) | 0.5% (1/223)
HDL Normal to Low ≥40 to <40 (mg/dL) (n/N*) | 10.7% (21/196) |  | 13.3% (18/135) |  | 14.7% (20/136) |  | 14.0% (45/322) |  | 7.4% (16/215) | 4.1% (4/97) | 5.1% (4/78) | 7.0% (29/417)
Fasting triglycerides Normal to High <150 to ≥200 (mg/dL) (n/N*) | 2.4% (4/167) |  | 7.0% (8/115) |  | 8.3% (9/108) |  | 7.7% (20/260) |  | 4.6% (7/153) | 8.2% (5/61) | 1.6% (1/64) | 6.2% (17/273)

N* = Number of subjects who had assessments at both Baseline and Endpoint.

§ Includes subjects treated with flexible dose of SAPHRIS 5 or 10 mg twice daily (N=90).

† Includes patients treated with flexible dose of SAPHRIS 5 or 10 mg twice daily (N=379)

In short-term schizophrenia trials, the proportion of patients with total cholesterol elevations ≥240 mg/dL (at Endpoint) was 8.3% for SAPHRIS-treated patients versus 7% for placebo-treated patients. The proportion of patients with elevations in triglycerides ≥200 mg/dL (at Endpoint) was 13.2% for SAPHRIS-treated patients versus 10.5% for placebo-treated patients. In short-term, placebo-controlled bipolar mania trials, the proportion of patients with total cholesterol elevations ≥240 mg/dL (at Endpoint) was 7.8% for SAPHRIS-treated patients versus 7.9% for placebo-treated patients. The proportion of patients with elevations in triglycerides ≥200 mg/dL (at Endpoint) was 13.1% for SAPHRIS-treated patients versus 8.6% for placebo-treated patients.

Pediatric Patients: Data from the short-term, placebo-controlled bipolar mania trial are presented in Table 4.

TABLE 4: Changes in Fasting Lipids in Pediatric Subjects
 | Bipolar I Disorder (3-weeks)
 | Placebo | SAPHRIS 2.5 mg twice daily | SAPHRIS 5 mg twice daily | SAPHRIS 10 mg twice daily
Mean Change from Baseline (mg/dL)
Total fasting cholesterol (N*) | -2.3 (57) | 3.7 (50) | 7.2 (57) | 9.3 (52)
Fasting LDL (N*) | -2.5 (57) | -0.2 (50) | 3.0 (57) | 4.9 (51)
Fasting HDL (N*) | 1.6 (57) | 2.3 (50) | 1.5 (57) | 1.7 (52)
Fasting triglycerides (N*) | -6.6 (57) | 8.7 (50) | 13.4 (57) | 14.7 (52)
Proportion of Subjects with Shifts from Baseline to Endpoint
Total fasting cholesterol Normal to High <170 to >=200 (mg/dL) (n/N*) | 1.8% (1/57) | 0% (0/50) | 1.8% (1/57) | 0% (0/52)
Fasting LDL Normal to High <110 to >=130 (n/N*) | 1.8% (1/57) | 2.0% (1/50) | 1.8% (1/57) | 0% (0/51)
Fasting HDL Normal to Low ≥40 to <40 (mg/dL) (n/N*) | 3.5% (2/57) | 6.0% (3/50) | 3.5% (2/57) | 9.6% (5/52)
Fasting triglycerides Normal to High <150 to ≥200 (mg/dL) (n/N*) | 0% (0/57) | 4.0% (2/50) | 3.5% (2/57) | 1.9% (1/52)

N* = Number of patients who had assessments at both Baseline and Endpoint

Weight Gain

Weight gain has been observed in patients treated with atypical antipsychotics, including SAPHRIS. Monitor weight at baseline and frequently thereafter.

Adult Patients: Pooled data on mean changes in body weight and the proportion of subjects meeting a weight gain criterion of ≥7% of body weight from the short-term, placebo-controlled schizophrenia and bipolar mania trials are presented in Table 5.

Table 5: Change in Body Weight in Adult Patients from Baseline
 | Schizophrenia (6-weeks) |  |  |  | Bipolar I Disorder (3-weeks)
 | Placebo | SAPHRIS |  |  | Placebo | SAPHRIS
 |  | 5 mg twice daily | 10 mg twice daily | 5 or 10 mg twice daily§ |  | 5 mg twice daily | 10 mg twice daily | 5 or 10 mg twice daily†
Change from Baseline (kg) (N*) | 0.0 (348) | 1.0 (251) | 0.9 (200) | 1.1 (532) | 0.2 (288) | 1.4 (110) | 1.3 (98) | 1.3 (544)
Proportion of Patients with a ≥7% Increase in Body Weight
% with ≥7% increase in body weight | 1.6% | 4.4% | 4.8% | 4.9% | 0.4% | 6.4% | 1.0% | 5.5%

N* = Number of subjects who had assessments at both Baseline and Endpoint.

§ Includes subjects treated with flexible dose of SAPHRIS 5 or 10 mg twice daily (N=90).

† Includes patients treated with flexible dose of SAPHRIS 5 or 10 mg twice daily (N=379).

Adult Patients: In a 52-week, double-blind, comparator-controlled adult trial that included primarily patients with schizophrenia, the mean weight gain from baseline was 0.9 kg. The proportion of patients with a ≥7% increase in body weight (at Endpoint) was 14.7%. Table 6 provides the mean weight change from baseline and the proportion of patients with a weight gain of ≥7% categorized by Body Mass Index (BMI) at baseline.

Table 6: Weight Change Results Categorized by BMI at Baseline: Comparator-Controlled 52-Week Study in Adults with Schizophrenia
 | BMI <23 SAPHRIS N=295 | BMI 23 - ≤27 SAPHRIS N=290 | BMI >27 SAPHRIS N=302
Mean change from Baseline (kg) | 1.7 | 1 | 0
% with ≥7% increase in body weight | 22% | 13% | 9%

Pediatric Patients: Data on mean changes in body weight and the proportion of pediatric patients meeting a weight gain criterion of ≥7% of body weight from the short-term, placebo-controlled bipolar mania trial are presented in Table 7. To adjust for normal growth, z-scores were derived (measured in standard deviations [SD]), which normalize for the natural growth of pediatric patients by comparisons to age- and sex-matched population standards.

The distance of a z-score from 0 represents the distance of a percentile from the median, measured in standard deviations (SD). After adjusting for age and sex, the mean change from baseline to endpoint in weight z-score for SAPHRIS 2.5 mg, 5 mg, and 10 mg twice daily, was 0.11, 0.08 and 0.09 SD versus 0.02 SD for placebo, respectively.

When treating pediatric patients, weight gain should be monitored and assessed against that expected for normal growth.

Table 7: Change in Body Weight in Pediatric Subjects from Baseline
 | Bipolar I Disorder (3-weeks)
 | Placebo | SAPHRIS 2.5 mg twice daily | SAPHRIS 5 mg twice daily | SAPHRIS 10 mg twice daily
Change from Baseline (kg) (N*) | 0.5 (89) | 1.7 (92) | 1.6 (90) | 1.4 (87)
 | Proportion of Subjects with a ≥7% Increase in Body Weight
% with ≥7% increase in body weight | 1.1% | 12.0% | 8.9% | 8.0%

N* = Number of subjects who had assessments at both Baseline and Endpoint.

5.6 Hypersensitivity Reactions

Hypersensitivity reactions have been observed in patients treated with SAPHRIS. In several cases, these reactions occurred after the first dose. These hypersensitivity reactions included: anaphylaxis, angioedema, hypotension, tachycardia, swollen tongue, dyspnea, wheezing and rash.

5.7 Orthostatic Hypotension, Syncope, and Other Hemodynamic Effects

Atypical antipsychotics cause orthostatic hypotension and syncope. Generally, the risk is greatest during initial dose titration and when increasing the dose. In short-term schizophrenia adult trials, syncope was reported in 0.2% (1/572) of patients treated with therapeutic doses (5 mg or 10 mg twice daily) of SAPHRIS, compared to 0.3% (1/378) of patients treated with placebo. In short-term bipolar mania adult trials, syncope was reported in 0.2% (1/620) of patients treated with therapeutic doses (5 mg or 10 mg twice daily) of SAPHRIS, compared to 0% (0/329) of patients treated with placebo. During adult pre-marketing clinical trials with SAPHRIS, including long-term trials without comparison to placebo, syncope was reported in 0.6% (11/1953) of patients treated with SAPHRIS. In a 3-week, bipolar mania pediatric trial, syncope was reported in 1% (1/104) of patients treated with SAPHRIS 2.5 mg twice daily, 1% (1/99) of patients treated with SAPHRIS 5 mg twice daily, and 0% (0/99) for patients treated with SAPHRIS 10 mg twice daily compared to 0% (0/101) for patients treated with placebo.

Orthostatic vital signs should be monitored in patients who are vulnerable to hypotension (elderly patients, patients with dehydration, hypovolemia, concomitant treatment with antihypertensive medications, patients with known cardiovascular disease (history of myocardial infarction or ischemic heart disease, heart failure, or conduction abnormalities), and patients with cerebrovascular disease. SAPHRIS should be used cautiously when treating patients who receive treatment with other drugs that can induce hypotension, bradycardia, respiratory or central nervous system depression [see Drug Interactions (7.1)]. Monitoring of orthostatic vital signs should be considered in all such patients, and a dose reduction should be considered if hypotension occurs.

5.8 Falls

SAPHRIS may cause somnolence, postural hypotension, motor and sensory instability, which may lead to falls and, consequently, fractures or other injuries. For patients with diseases, conditions, or medications that could exacerbate these effects, complete fall risk assessments when initiating antipsychotic treatment and recurrently for patients on long-term antipsychotic therapy.

5.9 Leukopenia, Neutropenia, and Agranulocytosis

In clinical trial and postmarketing experience, leukopenia and neutropenia have been reported temporally related to antipsychotic agents, including SAPHRIS. Agranulocytosis (including fatal cases) has been reported with other agents in the class.

Possible risk factors for leukopenia/neutropenia include pre-existing low white blood cell count (WBC) or absolute neutrophil count (ANC) and history of drug induced leukopenia/neutropenia. In patients with a pre-existing low WBC or ANC or a history of drug-induced leukopenia or neutropenia, perform a complete blood count (CBC) during the first few months of therapy. In such patients, consider discontinuation of SAPHRIS at the first sign of a clinically significant decline in WBC in the absence of other causative factors.

Monitor patients with clinically significant neutropenia for fever or other symptoms or signs of infection and treat promptly if such symptoms or signs occur. Discontinue SAPHRIS in patients with severe neutropenia (absolute neutrophil count <1000/mm^3) and follow their WBC until recovery.

5.10 QT Prolongation

The effects of SAPHRIS on the QT/QTc interval were evaluated in a dedicated adult QT study. This trial involved SAPHRIS doses of 5 mg, 10 mg, 15 mg, and 20 mg twice daily, and placebo, and was conducted in 151 clinically stable patients with schizophrenia, with electrocardiographic assessments throughout the dosing interval at baseline and steady state. At these doses, SAPHRIS was associated with increases in QTc interval ranging from 2 to 5 msec compared to placebo. No patients treated with SAPHRIS experienced QTc increases ≥60 msec from baseline measurements, nor did any patient experience a QTc of ≥500 msec.

Electrocardiogram (ECG) measurements were taken at various time points during the SAPHRIS clinical trial program (5 mg or 10 mg twice daily doses). Post-baseline QT prolongations exceeding 500 msec were reported at comparable rates for SAPHRIS and placebo in these short-term trials. There were no reports of Torsade de Pointes or any other adverse reactions associated with delayed ventricular repolarization.

The use of SAPHRIS should be avoided in combination with other drugs known to prolong QTc including Class 1A antiarrhythmics (e.g., quinidine, procainamide) or Class 3 antiarrhythmics (e.g., amiodarone, sotalol), antipsychotic medications (e.g., ziprasidone, chlorpromazine, thioridazine), and antibiotics (e.g., gatifloxacin, moxifloxacin). SAPHRIS should also be avoided in patients with a history of cardiac arrhythmias and in other circumstances that may increase the risk of the occurrence of torsade de pointes and/or sudden death in association with the use of drugs that prolong the QTc interval, including bradycardia; hypokalemia or hypomagnesemia; and presence of congenital prolongation of the QT interval.

5.11 Hyperprolactinemia

Like other drugs that antagonize dopamine D2 receptors, SAPHRIS can elevate prolactin levels, and the elevation can persist during chronic administration. Hyperprolactinemia may suppress hypothalamic GnRH, resulting in reduced pituitary gonadotropin secretion. This, in turn, may inhibit reproductive function by impairing gonadal steroidogenesis in both female and male patients. Galactorrhea, amenorrhea, gynecomastia, and impotence have been reported in patients receiving prolactin-elevating compounds. Long-standing hyperprolactinemia when associated with hypogonadism may lead to decreased bone density in both female and male subjects. In SAPHRIS adult pre-marketing clinical trials, the incidences of adverse events related to abnormal prolactin levels were 0.4% versus 0% for placebo. In a 3-week, bipolar mania pediatric trial, the incidence of adverse events related to abnormal prolactin levels were 0% in the SAPHRIS 2.5 mg twice daily treatment group, 2% in the SAPHRIS 5 mg twice daily treatment group, and 1% in the SAPHRIS 10 mg twice daily treatment group versus to 1% for patients treated with placebo [see Adverse Reactions (6.1)].

Tissue culture experiments indicate that approximately one-third of human breast cancers are prolactin-dependent in vitro, a factor of potential importance if the prescription of these drugs is considered in a patient with previously-detected breast cancer. Published epidemiologic studies have shown inconsistent results when exploring the potential association between hyperprolactinemia and breast cancer.

5.12 Seizures

Seizures were reported in 0% and 0.3% (0/572, 1/379) of adult patients treated with doses of 5 mg and 10 mg twice daily of SAPHRIS, respectively, compared to 0% (0/503, 0/203) of patients treated with placebo in pre-marketing short-term schizophrenia and bipolar mania trials, respectively. During adult pre-marketing clinical trials with SAPHRIS, including long-term trials without comparison to placebo, seizures were reported in 0.3% (5/1953) of patients treated with SAPHRIS. There were no reports of seizures in pediatric patients treated with SAPHRIS in a 3-week-term, bipolar mania trial.

As with other antipsychotic drugs, SAPHRIS should be used with caution in patients with a history of seizures or with conditions that potentially lower the seizure threshold. Conditions that lower the seizure threshold may be more prevalent in patients 65 years or older.

5.13 Potential for Cognitive and Motor Impairment

Somnolence was reported in patients treated with SAPHRIS. It was usually transient with the highest incidence reported during the first week of treatment. In short-term, fixed-dose, placebo-controlled schizophrenia adult trials, somnolence was reported in 15% (41/274) of patients on SAPHRIS 5 mg twice daily and in 13% (26/208) of patients on SAPHRIS 10 mg twice daily compared to 7% (26/378) of placebo patients. In short-term, placebo-controlled bipolar mania adult trials of therapeutic doses (5-10 mg twice daily), somnolence was reported in 23% (145/620) of patients on SAPHRIS compared to 5% (18/329) of placebo patients. In the 3-week fixed-dose study, somnolence occurred at a lower rate in the 5 mg twice daily dose 20% (24/122) versus the 10mg twice daily dose 26% (31/119) compared to 4% (5/126) in placebo patients. During adult pre-marketing clinical trials with SAPHRIS, including long-term trials without comparison to placebo, somnolence was reported in 18% (358/1953) of patients treated with SAPHRIS. Somnolence led to discontinuation in 0.6% (12/1953) of patients in short-term, placebo-controlled trials.

In a 3-week, placebo-controlled, bipolar I pediatric trial, the incidence of somnolence (including sedation and hypersomnia) for placebo, SAPHRIS 2.5 mg twice daily, 5 mg twice daily, and 10 mg twice daily, was 12% (12/101), 46% (48/104), 53% (52/99), and 49% (49/99), respectively. Somnolence led to discontinuation in 0%, 3%, 1%, and 2% of patients treated with placebo, and SAPHRIS 2.5 mg twice daily, 5 mg twice daily, and 10 mg twice daily, respectively.

Patients should be cautioned about operating hazardous machinery, including motor vehicles, until they are reasonably certain that SAPHRIS therapy does not affect them adversely.

5.14 Body Temperature Regulation

Atypical antipsychotics may disrupt the body’s ability to reduce core body temperature. In the pre-marketing short-term placebo-controlled trials for both schizophrenia and acute bipolar I disorder, the incidence of adverse reactions suggestive of body temperature increases was low (≤1%) and comparable to placebo (0%). During pre-marketing clinical trials with SAPHRIS, including long-term trials without comparison to placebo, the incidence of adverse reactions suggestive of body temperature increases (pyrexia and feeling hot) was ≤1%.

Strenuous exercise, exposure to extreme heat, dehydration, and anticholinergic medications may contribute to an elevation in core body temperature; use SAPHRIS with caution in patient who may experience these conditions.

5.15 Dysphagia

Esophageal dysmotility and aspiration have been associated with antipsychotic drug use. Dysphagia has been reported with SAPHRIS. SAPHRIS and other antipsychotic drugs should be used cautiously in patients at risk for aspiration.

6 ADVERSE REACTIONS

The following adverse reactions are discussed in more detail in other sections of the labeling:

- Use in Elderly Patients with Dementia-Related Psychosis [see Boxed Warning and Warnings and Precautions (5.1 and 5.2)]
- Neuroleptic Malignant Syndrome [see Warnings and Precautions (5.3)]
- Tardive Dyskinesia [see Warnings and Precautions (5.4)]
- Metabolic Changes [see Warnings and Precautions (5.5)]
- Hypersensitivity Reactions [see Contraindications, Warnings and Precautions (5.6)]
- Orthostatic Hypotension, Syncope, and other Hemodynamic Effects [see Warnings and Precautions (5.7)]
- Falls [see Warnings and Precautions (5.8)]
- Leukopenia, Neutropenia, and Agranulocytosis [see Warnings and Precautions (5.9)]
- QT Interval Prolongation [see Warnings and Precautions (5.10)]
- Hyperprolactinemia [see Warnings and Precautions (5.11)]
- Seizures [see Warnings and Precautions (5.12)]
- Potential for Cognitive and Motor Impairment [see Warnings and Precautions (5.13)]
- Body Temperature Regulation [see Warnings and Precautions (5.14)]
- Dysphagia [see Warnings and Precautions (5.15)]

The most common adverse reactions (≥5% and at least twice the rate of placebo) reported with acute treatment in adults with schizophrenia were akathisia, oral hypoesthesia, and somnolence. The safety profile of SAPHRIS in the maintenance treatment of schizophrenia in adults was similar to that seen with acute treatment.

The most common adverse reactions (≥5% and at least twice the rate of placebo) reported with acute monotherapy treatment of manic or mixed episodes associated with bipolar I disorder in adults were somnolence, oral hypoesthesia dizziness, extrapyramidal symptoms (excluding akathisia) and akathisia; and during the adjunctive therapy trial in bipolar I disorder in adults were somnolence and oral hypoesthesia. The rates were lower at the 5mg twice daily dose than the 10mg twice daily dose for all of these most common adverse reactions. The safety profile of SAPHRIS in the maintenance treatment of manic or mixed episodes associated with bipolar I disorder in adults was similar to that seen with acute treatment.

The adult information below is derived from a clinical trial database for SAPHRIS consisting of over 5355 patients and/or healthy subjects exposed to one or more sublingual doses of SAPHRIS. A total of 1427 SAPHRIS-treated patients were treated for at least 24 weeks and 785 SAPHRIS-treated patients had at least 52 weeks of exposure at therapeutic doses.

In a 3-week monotherapy trial, the most common adverse reactions (≥5% and at least twice the rate of placebo) reported in pediatric patients with bipolar I disorder treated with SAPHRIS were somnolence, dizziness, dysgeusia, oral hypoesthesia, nausea, increased appetite, fatigue, and increased weight. No new major safety findings were reported from a 50-week, open-label, uncontrolled safety trial.

A total of 651 pediatric patients were treated with SAPHRIS. Of these patients, 352 pediatric patients were treated with SAPHRIS for at least 180 days and 58 pediatric patients treated with SAPHRIS had at least 1 year of exposure. The safety of SAPHRIS was evaluated in 403 pediatric patients with bipolar I disorder who participated in a 3-week, placebo-controlled, double-blind trial, of whom 302 patients received SAPHRIS at fixed doses ranging from 2.5 mg to 10 mg twice daily.

The stated frequencies of adverse reactions represent the proportion of individuals who experienced a treatment-emergent adverse event of the type listed. A reaction was considered treatment emergent if it occurred for the first time or worsened while receiving therapy following baseline evaluation.

6.1 Clinical Trials Experience

Because clinical trials are conducted under widely varying conditions, adverse reaction rates observed in the clinical trials of a drug cannot be directly compared to rates in the clinical trials of another drug and may not reflect the rates observed in practice.

Adult Patients with Schizophrenia: The following findings are based on the short-term placebo-controlled pre-marketing trials for schizophrenia (a pool of three 6-week fixed-dose trials and one 6-week flexible-dose trial) in which sublingual SAPHRIS was administered in doses ranging from 5 to 10 mg twice daily.

Adverse Reactions Associated with Discontinuation of Treatment: A total of 9% of SAPHRIS-treated patients and 10% of placebo-treated patients discontinued due to adverse reactions. There were no drug-related adverse reactions associated with discontinuation in patients treated with SAPHRIS at the rate of at least 1% and at least twice the placebo rate.

Adverse Reactions Occurring at an Incidence of 2% or More in SAPHRIS-Treated Patients with Schizophrenia: Adverse reactions associated with the use of SAPHRIS (incidence of 2% or greater, rounded to the nearest percent, and SAPHRIS incidence greater than placebo) that occurred during acute therapy (up to 6-weeks in patients with schizophrenia) are shown in Table 8.

Table 8: Adverse Reactions Reported in 2% or More of Adult Patients in Any SAPHRIS Dose Group and Which Occurred at Greater Incidence Than in the Placebo Group in 6-Week Schizophrenia Trials
System Organ Class/ Preferred Term | Placebo N=378 % | SAPHRIS 5 mg twice daily N=274 % | SAPHRIS 10 mg twice daily N=208 % | All SAPHRIS§ 5 mg or 10 mg twice daily N=572 %
Gastrointestinal disorders
Constipation | 6 | 7 | 4 | 5
Dry mouth | 1 | 3 | 1 | 2
Oral hypoesthesia | 1 | 6 | 7 | 5
Salivary hypersecretion | 0 | <1 | 4 | 2
Stomach discomfort | 1 | <1 | 3 | 2
Vomiting | 5 | 4 | 7 | 5
General disorders
Fatigue | 3 | 4 | 3 | 3
Irritability | <1 | 2 | 1 | 2
Investigations
Increased weight | <1 | 2 | 2 | 3
Metabolism disorders
Increased appetite | <1 | 3 | 0 | 2
Nervous system disorders
Akathisia* | 3 | 4 | 11 | 6
Dizziness | 4 | 7 | 3 | 5
Extrapyramidal symptoms | 7 | 9 | 12 | 10
(excluding akathisia)†
Somnolence‡ | 7 | 15 | 13 | 13
Psychiatric disorders
Insomnia | 13 | 16 | 15 | 15
Vascular disorders
Hypertension | 2 | 2 | 3 | 2

* Akathisia includes: akathisia and hyperkinesia.

† Extrapyramidal symptoms included dystonia, oculogyration, dyskinesia, tardive dyskinesia, muscle rigidity, parkinsonism, tremor, and extrapyramidal disorder (excluding akathisia).

‡ Somnolence includes the following events: somnolence, sedation, and hypersomnia.

§ Also includes the Flexible-dose trial (N=90).

Dose-Related Adverse Reactions: In the short term schizophrenia trials the incidence of akathisia appeared to be dose-related (see Table 8).

Monotherapy in Adult Patients with Bipolar Mania: The following findings are based on the short-term placebo-controlled trials for bipolar mania (a pool of two 3-week flexible-dose trials and one 3-week fixed-dose trial) in which sublingual SAPHRIS was administered in doses of 5 mg or 10 mg twice daily.

Adverse Reactions Associated with Discontinuation of Treatment: Approximately 10% (61/620) of SAPHRIS-treated patients in short-term, placebo-controlled trials discontinued treatment due to an adverse reaction, compared with about 7% (22/329) on placebo. There were no adverse reactions associated with discontinuation in patients treated with SAPHRIS at the rate of at least 1% and at least twice the placebo rate

Adverse Reactions Occurring at an Incidence of 2% or More Among SAPHRIS-Treated (Monotherapy) patients with Bipolar I Disorder: Adverse reactions associated with the use of SAPHRIS (incidence of 2% or greater, rounded to the nearest percent, and SAPHRIS incidence greater than placebo) that occurred during acute monotherapy (up to 3-weeks in patients with bipolar mania) are shown in Table 9.

Table 9: Adverse Reactions Reported in 2% or More of Adult Patients in Any SAPHRIS Dose Group and Which Occurred at Greater Incidence Than in the Respective Placebo Group in 3-Week Bipolar Mania Fixed and Flexible Dose Trials
System Organ Class/Preferred Term | (Fixed Dose Study) |  |  | All Placeboa | All SAPHRIS 5 mg or 10 mg twice dailyb
 | Placebo | SAPHRIS 5 mg twice daily | SAPHRIS 10 mg twice daily
 | N=126 % | N=122 % | N=119 % | N=329 % | N=620 %
Gastrointestinal disorders
Oral Hypoesthesiac | 2 | 13 | 24 | 1 | 10
Nausea | 3 | 4 | 5 | 5 | 5
Constipation | 2 | 4 | 3 | 4 | 4
Dyspepsiah | 6 | 4 | 5 | 4 | 4
Vomiting | 2 | 1 | 3 | 3 | 3
Abdominal Paind | 0 | 2 | 3 | 3 | 3
Dry Mouth | 5 | 3 | 1 | 2 | 3
Toothache | 1 | 2 | 2 | 2 | 3
General disorders
Fatiguee | 2 | 2 | 5 | 2 | 4
Infections and Infestations
Nasopharyngitisi | 2 | 1 | 5 | 2 | 3
Investigations
Weight Increase | 1 | 0 | 1 | 1 | 3
Alanine Aminotransferase | 0 | 0 | 3 | 0 | 1
Increase
Metabolism disorders
Increased appetite | 2 | 1 | 6 | 2 | 4
Musculoskeletal and connective tissue disorders
Arthralgia | 1 | 1 | 2 | 1 | 2
Nervous system disorders
Somnolencef | 4 | 20 | 26 | 5 | 23
Dizziness | 5 | 3 | 5 | 4 | 8
Extrapyramidal symptoms | 7 | 7 | 11 | 4 | 8
(excluding akathisia)g
Akathisia | 1 | 4 | 15 | 2 | 6
Dysgeusia | 0 | 3 | 9 | <1 | 4
Psychiatric Disorders
Bipolar Disorder/Mania j | 3 | 8 | 3 | 5 | 6
Agitation | 1 | 4 | 3 | 3 | 4
Anxiety | 3 | 0 | 3 | 2 | 3

a Includes fixed and flexible dose trials

b SAPHRIS 5 mg to 10 mg twice daily with fixed and flexible dosing.

c Oral Hypoesthesia includes the preferred terms: oral hypoesthesia, oral paresthesia, and oral dysaesthesia.

d Abdominal pain includes the preferred terms: abdominal pain, abdominal pain upper, abdominal pain lower, and abdominal discomfort.

e Fatigue includes the preferred terms: fatigue and lethargy.

f Somnolence includes the preferred terms: somnolence, sedation, and hypersomnia.

g Extrapyramidal symptoms (excluding akathisia) includes the preferred terms: dyskinesia, dystonia, resting tremor, tremor, oromandibular dystonia, myoclonus, muscle spasms, muscle rigidity, musculoskeletal stiffness, muscle contractions involuntary, blepharospasm, tongue disorder, and Parkinsonism.

h Dyspepsia includes the preferred terms: dyspepsia and gastroesophageal reflux disease.

i Nasopharyngitis includes the preferred terms: nasopharyngitis and upper respiratory tract infection.

j Bipolar Disorder/Mania includes the preferred terms: bipolar disorder, bipolar I disorder and mania.

Monotherapy in Pediatric Patients with Bipolar Mania: The following findings are based on a 3-week , placebo-controlled trial for bipolar mania in which SAPHRIS was administered at doses of 2.5 mg, 5 mg, or 10 mg twice daily.

Adverse Reactions Leading to Discontinuation of Treatment: A total of 6.7% (7/104) of patients treated with SAPHRIS 2.5 mg twice daily, 5.1% (5/99) of patients treated with SAPHRIS 5 mg twice daily, and 5.1% (5/99) of patients treated with SAPHRIS 10 mg twice daily discontinued treatment due to adverse reactions compared to 4% (4/101) on placebo. The most common adverse reactions that led to discontinuation in pediatric patients treated with SAPHRIS (rates at least 2% in any SAPHRIS arm and at least twice the placebo rate) were somnolence (3% in the 2.5mg twice daily group, 1% in the 5mg twice daily group, and 2% in the 10mg twice daily group), abdominal pain (2% in the 10mg twice daily group), and nausea (2% in the 10mg twice daily group) No placebo-treated patients dropped out for these events.

Adverse Reactions Occurring with SAPHRIS at an Incidence of 2% or More in SAPHRIS-treated Bipolar I Patients: Adverse reactions associated with the use of SAPHRIS (incidence of ≥2% in any SAPHRIS dose group and greater than placebo) that occurred during acute therapy are shown in Table 10.

Table 10: Adverse Reactions Reported in 2% or More of Pediatric Patients (Ages 10 to 17 Years) in Any SAPHRIS Dose Group and Which Occurred at Greater Incidence Than in the Placebo Group in a 3-Week Bipolar Mania Trial
System Organ Class/ AE Preferred Term | Placebo | SAPHRIS 2.5 mg twice daily | SAPHRIS 5 mg twice daily | SAPHRIS 10 mg twice daily | All SAPHRIS 2.5, 5, and 10 mg
 | N=101 % | N=104 % | N=99 % | N=99 % | N=302 %
Cardiac Disorders
Tachycardia^1 | 0 | 3 | 0 | 1 | 1
Gastrointestinal Disorders
Oral hypoesthesia^2 | 4 | 25 | 25 | 30 | 27
Nausea | 3 | 6 | 6 | 6 | 6
Vomiting | 3 | 4 | 4 | 4 | 4
Abdominal pain^3 | 7 | 9 | 3 | 5 | 6
Glossodynia | 0 | 0 | 2 | 0 | 1
General Disorders and Administrative Site Disorders
Fatigue^4 | 5 | 4 | 8 | 14 | 9
Irritability | 1 | 1 | 1 | 2 | 1
Injury, Poisoning, and Procedural Complications
Muscle strain | 0 | 0 | 0 | 2 | 1
Investigations
Increased weight | 0 | 6 | 2 | 2 | 3
Hyperinsulinemia^5 | 0 | 1 | 3 | 1 | 2
ALT increased | 0 | 0 | 0 | 2 | 1
AST increased | 0 | 0 | 0 | 2 | 1
Metabolism and Nutrition Disorders
Increased appetite | 2 | 10 | 9 | 6 | 8
Dehydration | 1 | 0 | 2 | 0 | 1
Musculoskeletal and Connective Tissue Disorders
Myalgia | 0 | 0 | 2 | 1 | 1
Nervous System Disorders
Somnolence^6 | 12 | 46 | 53 | 49 | 49
Headache | 6 | 8 | 11 | 9 | 9
Dizziness | 3 | 6 | 10 | 5 | 7
Dysgeusia | 2 | 4 | 5 | 9 | 6
Akathisia | 0 | 2 | 2 | 1 | 2
Parkinsonism | 0 | 1 | 0 | 2 | 1
Psychiatric Disorders
Insomnia | 3 | 3 | 4 | 3 | 3
Suicidal ideation | 1 | 4 | 1 | 3 | 3
Anger | 0 | 0 | 0 | 2 | 1
Reproductive System and Breast Disorders
Dysmenorrhea | 1 | 0 | 2 | 0 | 1
Respiratory, Thoracic, and Mediastinal Disorders
Oropharyngeal pain | 2 | 0 | 3 | 1 | 1
Nasal congestion | 1 | 0 | 2 | 0 | 1
Dyspnea | 0 | 0 | 2 | 0 | 1
Skin and Subcutaneous Tissue Disorders
Rash | 1 | 0 | 1 | 2 | 1

^1 Includes the preferred terms tachycardia and heart rate increased.

^2 Includes the preferred terms oral hypoesthesia, oral paresthesia, and oral dysesthesia.

^3 Includes the preferred terms abdominal pain, abdominal pain upper, abdominal pain lower, and abdominal discomfort.

^4 Includes the preferred terms fatigue and lethargy.

^5 Includes the preferred terms hyperinsulinemia and blood insulin increased.

^6 Includes the preferred terms somnolence, sedation, and hypersomnia.

Dose-Related Adverse Reactions: In the short term pediatric bipolar I trial the incidence of fatigue appeared to be dose-related (see Table 10).

Adjunctive Therapy in Adult Patients with Bipolar Mania: The following findings are based on a 12 week placebo-controlled trial (with a 3 week efficacy endpoint) in adult patients with bipolar mania in which sublingual SAPHRIS was administered in doses of 5 mg or 10 mg twice daily as adjunctive therapy with lithium or valproate.

Adverse Reactions Associated with Discontinuation of Treatment: Approximately 16% (25/158) of SAPHRIS-treated patients discontinued treatment due to an adverse reaction, compared with about 11% (18/166) on placebo. The most common adverse reactions associated with discontinuation in subjects treated with SAPHRIS (rates at least 1% and at least twice the placebo rate) were depression (2.5%), suicidal ideation (2.5%), bipolar I disorder (1.9%), insomnia (1.9%) and depressive symptoms (1.3%).

Adverse Reactions Occurring at an Incidence of 2% or More Among SAPHRIS-Treated (Adjunctive) Bipolar I Patients: Adverse reactions associated with the use of SAPHRIS (incidence of 2% or greater, rounded to the nearest percent, and SAPHRIS incidence greater than placebo) that occurred during acute adjunctive therapy at 3 weeks, a time when most of the patients were still participating in the trial, are shown in Table 11.

Table 11: Adverse Reactions Reported in 2% or More of Adult Patients In Any SAPHRIS-Dose Group and Which Occurred at Greater Incidence Than in the Placebo Group at 3 Weeks in Adjunctive Bipolar Mania Trials
System Organ Class/Preferred Term | Placebo N=166 % | SAPHRIS 5 mg or 10 mg twice daily* N=158 %
Gastrointestinal disorders
Dyspepsia | 2 | 3
Oral hypoesthesia | 0 | 5
General disorders
Fatigue | 2 | 4
Edema peripheral | <1 | 3
Investigations
Increased weight | 0 | 3
Nervous system disorders
Dizziness | 2 | 4
Other extrapyramidal symptoms (excluding akathisia)† | 5 | 6
Somnolence‡ | 10 | 22
Psychiatric disorders
Insomnia | 8 | 10
Vascular disorders
Hypertension | <1 | 3

* SAPHRIS 5 mg to 10 mg twice daily with flexible dosing.

† Extrapyramidal symptoms included: dystonia, parkinsonism, oculogyration, and tremor (excluding akathisia).

‡ Somnolence includes the following events: somnolence and sedation.

Dystonia: Symptoms of dystonia, prolonged abnormal contractions of muscle groups, may occur in susceptible individuals during the first few days of treatment. Dystonic symptoms include: spasm of the neck muscles, sometimes progressing to tightness of the throat, swallowing difficulty, difficulty breathing, and/or protrusion of the tongue. While these symptoms can occur at low doses, they occur more frequently and with greater severity with high potency and at higher doses of first generation antipsychotic drugs. An elevated risk of acute dystonia is observed in males and younger age groups [see Dosage and Administration (2.3), Use in Specific Populations (8.4), and Clinical Pharmacology (12.3)].

Extrapyramidal Symptoms: In the short-term, placebo-controlled schizophrenia and bipolar mania adult trials, data was objectively collected on the Simpson Angus Rating Scale for extrapyramidal symptoms (EPS), the Barnes Akathisia Scale (for akathisia) and the Assessments of Involuntary Movement Scales (for dyskinesias). The mean change from baseline for the all-SAPHRIS 5 mg or 10 mg twice daily treated group was comparable to placebo in each of the rating scale scores.

In the short-term, placebo-controlled schizophrenia adult trials, the incidence of reported EPS-related events, excluding events related to akathisia, for SAPHRIS-treated patients was 10% versus 7% for placebo; and the incidence of akathisia-related events for SAPHRIS-treated patients was 6% versus 3% for placebo. In short-term placebo-controlled bipolar mania adult trials, the incidence of EPS-related events, excluding events related to akathisia, for SAPHRIS-treated patients was 8% versus 4% for placebo; and the incidence of akathisia-related events for SAPHRIS-treated patients was 7% versus 3% for placebo. The incidence rates of all EPS events (including akathisia) were lower at the 5mg twice daily dose (11% of N=122) than the 10mg twice daily dose (25% of N=119) in a fixed-dose study.

In a 3-week, placebo-controlled pediatric trial with bipolar I disorder, the incidences of EPS-related events, excluding events related to akathisia, were 4%, 3%, and 5% for patients treated with SAPHRIS 2.5 mg, 5 mg, and 10 mg twice daily, respectively, as compared to 3% for placebo-treated patients. EPS-related events include: bradykinesia, dyskinesia, dystonia, oromandibular dystonia, muscle contractions involuntary, muscle twitching, musculoskeletal stiffness, parkinsonism, protrusion tongue, resting tremor, and tremor.

For events of akathisia, incidences were 2%, 2%, and 1% for pediatric patients treated with SAPHRIS 2.5 mg, 5 mg, and 10 mg twice daily, respectively, as compared to 0% for placebo-treated patients.

Other Findings: Oral hypoesthesia and/or oral paresthesia may occur directly after administration of SAPHRIS and usually resolves within 1 hour.

Laboratory Test Abnormalities:

Transaminases: Transient elevations in serum transaminases (primarily ALT) in the short-term schizophrenia and bipolar mania adult trials were more common in treated patients. In short-term, placebo-controlled schizophrenia adult trials, the mean increase in transaminase levels for SAPHRIS-treated patients was 1.6 units/L compared to a decrease of 0.4 units/L for placebo-treated patients. The proportion of patients with transaminase elevations ≥3 times ULN (at Endpoint) was 0.9% for SAPHRIS-treated patients versus 1.3% for placebo-treated patients. In short-term, placebo-controlled bipolar mania adult trials, the mean increase in transaminase levels for SAPHRIS-treated patients was 6.1 units/L compared to a decrease of 3.9 units/L in placebo-treated patients. The proportion of patients with transaminase elevations ≥3 times upper limit of normal (ULN) (at Endpoint) was 2.1% for SAPHRIS-treated patients versus 0.7% for placebo-treated patients. The incidence rate of transaminase elevations ≥3 times ULN is 3% of N=95 for 10 mg twice daily dose, and 0% of N=108 for the 5 mg twice daily dose and 0% of N=115 for placebo in a fixed-dose study.

In a 52-week, double-blind, comparator-controlled trial that included primarily adult patients with schizophrenia, the mean increase from baseline of ALT was 1.7 units/L.

In a 3-week, placebo-controlled pediatric trial with bipolar I disorder, transient elevations in serum transaminases (primarily ALT) were more common in treated patients. The proportion of pediatric patients with ALT elevations ≥3 times upper limit of normal (ULN) was 2.4% for patients treated with SAPHRIS 10 mg twice daily versus none for the other SAPHRIS dose groups and placebo-treated patients.

Prolactin: In short-term, placebo-controlled adult schizophrenia trials, the mean decreases in prolactin levels were 6.5 ng/mL for SAPHRIS-treated patients compared to 10.7 ng/mL for placebo-treated patients. The proportion of patients with prolactin elevations ≥4 times ULN (at Endpoint) were 2.6% for SAPHRIS-treated patients versus 0.6% for placebo-treated patients. In short-term, placebo-controlled bipolar mania adult trials, the mean increase in prolactin levels was 6.7 ng/mL for SAPHRIS-treated patients compared to a decrease of 1.0 ng/mL for placebo-treated patients. The proportion of patients with prolactin elevations ≥4 times ULN (at Endpoint) were 2.0% for SAPHRIS-treated patients versus 0.8% for placebo-treated patients.

In a long-term (52-week), double-blind, comparator-controlled adult trial that included primarily patients with schizophrenia, the mean decrease in prolactin from baseline for SAPHRIS-treated patients was 26.9 ng/mL.

In a 3-week, placebo-controlled pediatric trial with bipolar I disorder, the mean increases (at Endpoint) in prolactin levels were 3.2 ng/mL for patients treated with SAPHRIS 2.5 mg twice daily, 2.1 ng/mL for patients treated with SAPHRIS 5 mg twice daily, and 6.4 ng/mL for patients treated with SAPHRIS 10 mg twice daily compared to an increase of 2.5 ng/mL for placebo-treated patients. There were no reports of prolactin elevations ≥4 times ULN (at Endpoint) for patients treated with SAPHRIS or placebo. Galactorrhea or dysmenorrhea were reported in 0% of patients treated with SAPHRIS 2.5 mg twice daily, 2% of patients treated with SAPHRIS 5 mg twice daily, and 1% of patients treated with SAPHRIS 10 mg twice daily compared to 1% of placebo-treated patients. There were no reports of gynecomastia in this trial.

Creatine Kinase (CK): The proportion of adult patients with CK elevations >3 times ULN at any time were 6.4% and 11.1% for patients treated with SAPHRIS 5 mg twice daily and 10 mg twice daily, respectively, as compared to 6.7% for placebo-treated patients in pre-marketing short-term, fixed-dose trials in schizophrenia and bipolar mania. The clinical relevance of this finding is unknown.

The proportion of patients with CK elevations ≥3 times ULN during a 3-week trial in pediatric bipolar I disorder at any time were 1%, 0%, and 1% for patients treated with SAPHRIS 2.5 mg, 5 mg, and 10 mg twice daily, respectively, versus 3% for placebo-treated patients.

Other Adverse Reactions Observed During the Premarketing Evaluation of SAPHRIS: Following is a list of MedDRA terms that reflect adverse reactions reported by patients treated with sublingual SAPHRIS at multiple doses of ≥5 mg twice daily during any phase of a trial within the database of adult patients. The reactions listed are those that could be of clinical importance, as well as reactions that are plausibly drug-related on pharmacologic or other grounds. Reactions already listed for either adults or pediatric patients in other parts of Adverse Reactions (6), or those considered in Contraindications (4), Warnings and Precautions (5) or Overdosage (10) are not included. Reactions are further categorized by MedDRA system organ class and listed in order of decreasing frequency according to the following definitions: those occurring in at least 1/100 patients (frequent) (only those not already listed in the tabulated results from placebo-controlled trials appear in this listing); those occurring in 1/100 to 1/1000 patients (infrequent); and those occurring in fewer than 1/1000 patients (rare).

Blood and lymphatic disorders: infrequent: anemia; rare: thrombocytopenia

Cardiac disorders: infrequent: temporary bundle branch block

Eye disorders: infrequent: accommodation disorder

Gastrointestinal disorders: infrequent: swollen tongue

General disorders: rare: idiosyncratic drug reaction

Investigations: infrequent: hyponatremia

Nervous system disorders: infrequent: dysarthria

Following is a list of MedDRA terms not already listed either for adults or pediatric patients in other parts of Adverse Reactions (6), or those considered in Contraindications (4), Warnings and Precautions (5) or Overdosage (10) that reflect adverse reactions reported by pediatric patients (Ages 10 to 17 years) treated with sublingual SAPHRIS at doses of 2.5 mg, 5 mg, or 10 mg twice daily during any phase of a trial within the database of pediatric patients.

Eye disorders: infrequent: diplopia, vision blurred

Gastrointestinal disorders: infrequent: gastroesophageal reflux disease

Injury, Poisoning, and Procedural Complications: infrequent: fall

Skin and subcutaneous tissue disorders: infrequent: photosensitivity reaction

Renal and urinary disorders: infrequent: enuresis

6.2 Postmarketing Experience

The following adverse reactions have been identified during post-approval use of SAPHRIS. Because these reactions are reported voluntarily from a population of uncertain size, it is not always possible to establish a causal relationship to drug exposure. In many cases, the occurrence of these adverse reactions led to discontinuation of therapy.

- Application site reactions, primarily in the sublingual area, have been reported. These application site reactions included oral ulcers, blisters, peeling/sloughing, and inflammation.
- Choking has been reported by patients, some of whom may have also experienced oropharyngeal muscular dysfunction or hypoesthesia.

7 DRUG INTERACTIONS

7.1 Drugs Having Clinically Important Drug Interactions with SAPHRIS

Table 12: Clinically Important Drug Interactions with SAPHRIS
Concomitant Drug Name or Drug Class | Clinical Rationale | Clinical Recommendation
Antihypertensive Drugs | Because of its α1-adrenergic antagonism with potential for inducing hypotension, SAPHRIS may enhance the effects of certain antihypertensive agents [see Warnings and Precautions (5.7)]. | Monitor blood pressure and adjust dosage of antihypertensive drug accordingly.
Strong CYP1A2 Inhibitors (e.g., Fluvoxamine) | SAPHRIS is metabolized by CYP1A2. Marginal increase of asenapine exposure was observed when SAPHRIS is used with fluvoxamine at 25 mg administered twice daily [see Clinical Pharmacology (12.3)]. However, the tested fluvoxamine dose was suboptimal. Full therapeutic dose of fluvoxamine is expected to cause a greater increase in asenapine exposure. | Dosage reduction for SAPHRIS based on clinical response may be necessary.
CYP2D6 substrates and inhibitors (e.g., paroxetine) | SAPHRIS may enhance the inhibitory effects of paroxetine on its own metabolism. Concomitant use of paroxetine with SAPHRIS increased the paroxetine exposure by 2-fold as compared to use paroxetine alone [see Clinical Pharmacology (12.3)]. | Reduce paroxetine dose by half when paroxetine is used in combination with SAPHRIS.

7.2 Drugs Having No Clinically Important Interactions with SAPHRIS

No dosage adjustment of SAPHRIS is necessary when administered concomitantly with paroxetine (see Table 12 in Drug Interactions (7.1) for paroxetine dosage adjustment), imipramine, cimetidine, valproate, lithium, or a CYP3A4 inducer (e.g., carbamazepine, phenytoin, rifampin).

In addition, valproic acid and lithium pre-dose serum concentrations collected from an adjunctive therapy study were comparable between asenapine-treated patients and placebo-treated patients indicating a lack of effect of asenapine on valproic and lithium plasma levels.

8 USE IN SPECIFIC POPULATIONS

8.1 Pregnancy

Pregnancy Exposure Registry

There is a pregnancy exposure registry that monitors pregnancy outcomes in women exposed to SAPHRIS during pregnancy. For more information contact the National Pregnancy Registry for Atypical Antipsychotics at 1-866-961-2388 or visit http://womensmentalhealth.org/clinical-and-research-programs/pregnancyregistry/.

Risk Summary

Neonates exposed to antipsychotic drugs during the third trimester of pregnancy are at risk for extrapyramidal and/or withdrawal symptoms. Studies have not been conducted with SAPHRIS in pregnant women. There are no available human data informing the drug-associated risk. The background risk of major birth defects and miscarriage for the indicated populations are unknown. However, the background risk in the U.S. general population of major birth defects is 2-4% and of miscarriage is 15-20% of clinically recognized pregnancies. No teratogenicity was observed in animal reproduction studies with intravenous administration of asenapine to rats and rabbits during organogenesis at doses 0.7 and 0.4 times, respectively, the maximum recommended human dose (MRHD) of 10 mg sublingually twice daily. In a pre-and post-natal study in rats, intravenous administration of asenapine at doses up to 0.7 times the MRHD produced increases in post-implantation loss and early pup deaths, and decreases in subsequent pup survival and weight gain [see Data]. Advise pregnant women of the potential risk to a fetus.

Clinical Considerations

Fetal/Neonatal Adverse Reactions

Extrapyramidal and/or withdrawal symptoms, including agitation, hypertonia, hypotonia, tremor, somnolence, respiratory distress and feeding disorder have been reported in neonates who were exposed to antipsychotic drugs during the third trimester of pregnancy. These symptoms have varied in severity. Some neonates recovered within hours or days without specific treatment; others required prolonged hospitalization. Monitor neonates for extrapyramidal and/or withdrawal symptoms and manage symptoms appropriately.

Data

Animal Data

In animal studies, asenapine increased post-implantation loss and decreased pup weight and survival at doses similar to or less than recommended clinical doses. In these studies there was no increase in the incidence of structural abnormalities caused by asenapine.

Asenapine was not teratogenic in reproduction studies in rats and rabbits at intravenous doses up to 1.5 mg/kg in rats and 0.44 mg/kg in rabbits administered during organogenesis. These doses are 0.7 and 0.4 times, respectively, the maximum recommended human dose (MRHD) of 10 mg twice daily given sublingually on a mg/m^2 basis. Plasma levels of asenapine were measured in the rabbit study, and the area under the curve (AUC) at the highest dose tested was 2 times that in humans receiving the MRHD.

In a study in which rats were treated from day 6 of gestation through day 21 postpartum with intravenous doses of asenapine of 0.3, 0.9, and 1.5 mg/kg/day (0.15, 0.4, and 0.7 times the MRHD of 10 mg twice daily given sublingually on a mg/m^2 basis), increases in post-implantation loss and early pup deaths were seen at all doses, and decreases in subsequent pup survival and weight gain were seen at the two higher doses. A cross-fostering study indicated that the decreases in pup survival were largely due to prenatal drug effects. Increases in post-implantation loss and decreases in pup weight and survival were also seen when pregnant rats were dosed orally with asenapine.

8.2 Lactation

Risk Summary

Lactation studies have not been conducted to assess the presence of asenapine in human milk, the effects of asenapine on the breastfed infant, or the effects of asenapine on milk production. Asenapine is excreted in rat milk. The development and health benefits of breastfeeding should be considered along with the mother’s clinical need for SAPHRIS and any potential adverse effects on the breastfed infant from SAPHRIS or from the underlying maternal condition.

8.4 Pediatric Use

Safety and efficacy of SAPHRIS in pediatric patients below the age of 10 years of age have not been evaluated.

Bipolar I Disorder

The safety and efficacy of SAPHRIS as monotherapy in the treatment of bipolar I disorder were established in a 3-week, placebo-controlled, double-blind trial of 403 pediatric patients 10 to 17 years of age, of whom 302 patients received SAPHRIS at fixed doses ranging from 2.5 mg to 10 mg twice daily [see Dosage and Administration (2.3), Adverse Reactions (6.1), Clinical Pharmacology (12.3), and Clinical Studies (14.2)]. In a Phase 1 study, pediatric patients aged 10 to 17 years appeared to be more sensitive to dystonia with initial dosing with asenapine when the recommended dose escalation schedule was not followed. Similar safety findings were reported from a 50-week, open-label, uncontrolled safety trial in pediatric patients with bipolar I disorder treated with SAPHRIS monotherapy. The safety and efficacy of SAPHRIS as adjunctive therapy in the treatment of bipolar I disorder have not been established in the pediatric population. In general, the pharmacokinetics of asenapine in pediatric patients (10 to 17 years) and adults are similar [see Clinical Pharmacology (12.3)].

Schizophrenia

Efficacy of SAPHRIS was not demonstrated in an 8-week, placebo-controlled, double-blind trial, in 306 adolescent patients aged 12 to 17 years with schizophrenia at doses of 2.5 and 5 mg twice daily. The most common adverse reactions (proportion of patients equal or greater than 5% and at least twice placebo) reported were somnolence, akathisia, dizziness, and oral hypoesthesia or paresthesia. The proportion of patients with an equal or greater than 7% increase in body weight at endpoint compared to baseline for placebo, SAPHRIS 2.5 mg twice daily, and SAPHRIS 5 mg twice daily was 3%, 10%, and 10%, respectively.

The clinically relevant adverse reactions identified in the pediatric schizophrenia trial were generally similar to those observed in the pediatric bipolar I and adult bipolar I and schizophrenia trials. No new major safety findings were reported from a 26-week, open-label, uncontrolled safety trial in pediatric patients with schizophrenia treated with SAPHRIS monotherapy.

Juvenile Animal Data

Subcutaneous administration of asenapine to juvenile rats for 56 days from day 14 of age to day 69 of age at 0.4, 1.2, and 3.2 mg/kg/day (0.2, 0.6 and 1.5 times the maximum recommended human dose of 10 mg twice daily given sublingually on a mg/m^2 basis) resulted in significant reduction in body weight gain in animals of both sexes at all dose levels from the start of dosing until weaning. Body weight gain remained reduced in males to the end of treatment, however, recovery was observed once treatment ended. Neurobehavioral assessment indicated increased motor activity in animals at all dose levels following the completion of treatment, with the evidence of recovery in males. There was no recovery after the end of treatment in female activity pattern as late as day 30 following the completion of treatment (last retesting). Therefore, a No Observed Adverse Effect Level (NOAEL) for the juvenile animal toxicity of asenapine could not be determined. There were no treatment-related effects on the startle response, learning/memory, organ weights, microscopic evaluations of the brain and, reproductive performance (except for minimally reduced conception rate and fertility index in males and females administered 1.2 and 3.2 mg/kg/day).

8.5 Geriatric Use

Clinical studies of SAPHRIS in the treatment of schizophrenia and bipolar mania did not include sufficient numbers of patients aged 65 and over to determine whether or not they respond differently than younger patients. Of the approximately 2250 patients in pre-marketing clinical studies of SAPHRIS, 1.1% (25) were 65 years of age or over. Multiple factors that might increase the pharmacodynamic response to SAPHRIS, causing poorer tolerance or orthostasis, could be present in elderly patients, and these patients should be monitored carefully. Based on a pharmacokinetic study in elderly patients, dosage adjustments are not recommended based on age alone [see Clinical Pharmacology (12.3)].

Elderly patients with dementia-related psychosis treated with SAPHRIS are at an increased risk of death compared to placebo. SAPHRIS is not approved for the treatment of patients with dementia-related psychosis [see Boxed Warning].

8.6 Renal Impairment

No dosage adjustment for SAPHRIS is required on the basis of a patient’s renal function (mild to severe renal impairment, glomerular filtration rate between 15 and 90 mL/minute). The exposure of asenapine was similar among subjects with varying degrees of renal impairment and subjects with normal renal function [see Clinical Pharmacology (12.3)]. The effect of renal function on the excretion of other metabolites and the effect of dialysis on the pharmacokinetics of asenapine has not been studied.

8.7 Hepatic Impairment

SAPHRIS is contraindicated in patients with severe hepatic impairment (Child-Pugh C) because asenapine exposure is 7-fold higher in subjects with severe hepatic impairment than the exposure observed in subjects with normal hepatic function.

No dosage adjustment for SAPHRIS is required in patients with mild to moderate hepatic impairment (Child-Pugh A and B) because asenapine exposure is similar to that in subjects with normal hepatic function [see Contraindications (4) and Clinical Pharmacology (12.3)].

8.8 Other Specific Populations

No dosage adjustment for SAPHRIS is required on the basis of a patient’s sex, race (Caucasian and Japanese), or smoking status [see Clinical Pharmacology (12.3)].

9 DRUG ABUSE AND DEPENDENCE

9.1 Controlled Substance

SAPHRIS is not a controlled substance.

9.2 Abuse

SAPHRIS has not been systematically studied in animals or humans for its abuse potential or its ability to induce tolerance or physical dependence. Thus, it is not possible to predict the extent to which a CNS-active drug will be misused, diverted and/or abused once it is marketed. Patients should be evaluated carefully for a history of drug abuse, and such patients should be observed carefully for signs that they are misusing or abusing SAPHRIS (e.g., drug-seeking behavior, increases in dose).

10 OVERDOSAGE

Human Experience: In adult pre-marketing clinical studies involving more than 3350 patients and/or healthy subjects, accidental or intentional acute overdosage of SAPHRIS was identified in 3 patients. Among these few reported cases of overdose, the highest estimated ingestion of SAPHRIS was 400 mg. Reported adverse reactions at the highest dosage included agitation and confusion.

Management of Overdosage: There is no specific antidote to SAPHRIS. The possibility of multiple drug involvement should be considered. An electrocardiogram should be obtained and management of overdose should concentrate on supportive therapy, maintaining an adequate airway, oxygenation and ventilation, and management of symptoms. Consult with a Certified Poison Control Center for up-to-date guidance and advice on the management of overdosage (1-800-222-1222.)

Hypotension and circulatory collapse should be treated with appropriate measures, such as intravenous fluids and/or sympathomimetic agents (epinephrine and dopamine should not be used, since beta stimulation may worsen hypotension in the setting of SAPHRIS-induced alpha blockade). In case of severe extrapyramidal symptoms, anticholinergic medication should be administered. Close medical supervision and monitoring should continue until the patient recovers.

11 DESCRIPTION

SAPHRIS contains asenapine maleate which is an atypical antipsychotic that is available for sublingual administration. Asenapine belongs to the class dibenzo-oxepino pyrroles. The chemical designation is (3aRS,12bRS)-5-Chloro-2-methyl-2,3,3a,12b-tetrahydro-1Hdibenzo[2,3:6,7]oxepino[4,5-c]pyrrole (2Z)-2-butenedioate (1:1). Its molecular formula is C17H16ClNO•C4H4O4 and its molecular weight is 401.84 (free base: 285.8). The chemical structure is:

Asenapine maleate is a white to off-white powder.

SAPHRIS, black cherry flavor, is supplied for sublingual administration in tablets containing 2.5 mg, 5 mg or 10 mg asenapine; inactive ingredients include gelatin, mannitol, sucralose, and black cherry flavor.

12 CLINICAL PHARMACOLOGY

12.1 Mechanism of Action

The mechanism of action of asenapine, in schizophrenia and bipolar I disorder, is unknown. It has been suggested that the efficacy of asenapine in schizophrenia could be mediated through a combination of antagonist activity at D2 and 5-HT2A receptors.

12.2 Pharmacodynamics

Asenapine exhibits high affinity for serotonin 5-HT1A, 5-HT1B, 5-HT2A, 5-HT2B, 5-HT2C, 5-HT5A, 5-HT6, and 5-HT7 receptors (Ki values of 2.5, 2.7, 0.07, 0.18, 0.03, 1.6, 0.25, and 0.11 nM, respectively), dopamine D2A, D2B, D3, D4, and D1 receptors (Ki values of 1.3, 1.4, 0.42, 1.1, and 1.4 nM, respectively), α1A, α2A, α2B, and α2C -adrenergic receptors (Ki values of 1.2, 1.2, 0.33 and 1.2 nM, respectively), and histamine H1 receptors (Ki value 1.0 nM), and moderate affinity for H2 receptors (Ki value of 6.2 nM). In in vitro assays asenapine acts as an antagonist at these receptors. Asenapine has no appreciable affinity for muscarinic cholinergic receptors (e.g., Ki value of 8128 nM for M1).

12.3 Pharmacokinetics

Following a single 5 mg dose of SAPHRIS, the mean Cmax was approximately 4 ng/mL and was observed at a mean tmax of 1 hour. Elimination of asenapine is primarily through direct glucuronidation by UGT1A4 and oxidative metabolism by cytochrome P450 isoenzymes (predominantly CYP1A2). Following an initial more rapid distribution phase, the mean terminal half-life is approximately 24 hrs. With multiple-dose twice-daily dosing, steady-state is attained within 3 days. Overall, steady-state asenapine pharmacokinetics are similar to single-dose pharmacokinetics.

Absorption: Following sublingual administration, asenapine is rapidly absorbed with peak plasma concentrations occurring within 0.5 to 1.5 hours. The absolute bioavailability of sublingual asenapine at 5 mg is 35%. Increasing the dose from 5 mg to 10 mg twice daily (a two-fold increase) results in less than linear (1.7 times) increases in both the extent of exposure and maximum concentration. The absolute bioavailability of asenapine when swallowed is low (<2% with an oral tablet formulation).

The intake of water several (2 or 5) minutes after asenapine administration resulted in decreased asenapine exposure. Therefore, eating and drinking should be avoided for 10 minutes after administration [see Dosage and Administration (2.1)].

Distribution: Asenapine is rapidly distributed and has a large volume of distribution (approximately 20 - 25 L/kg), indicating extensive extravascular distribution. Asenapine is highly bound (95%) to plasma proteins, including albumin and α1-acid glycoprotein.

Metabolism and Elimination: Direct glucuronidation by UGT1A4 and oxidative metabolism by cytochrome P450 isoenzymes (predominantly CYP1A2) are the primary metabolic pathways for asenapine.

Asenapine is a high clearance drug with a clearance after intravenous administration of 52 L/h. In this circumstance, hepatic clearance is influenced primarily by changes in liver blood flow rather than by changes in the intrinsic clearance, i.e., the metabolizing enzymatic activity. Following an initial more rapid distribution phase, the terminal half-life of asenapine is approximately 24 hours. Steady-state concentrations of asenapine are reached within 3 days of twice daily dosing.

After administration of a single dose of [^14C]-labeled asenapine, about 90% of the dose was recovered; approximately 50% was recovered in urine, and 40% recovered in feces. About 50% of the circulating species in plasma have been identified. The predominant species was asenapine N^+-glucuronide; others included N-desmethylasenapine, N-desmethylasenapine N-carbamoyl glucuronide, and unchanged asenapine in smaller amounts. SAPHRIS activity is primarily due to the parent drug.

In vitro studies indicate that asenapine is a substrate for UGT1A4, CYP1A2 and to a lesser extent CYP3A4 and CYP2D6. Asenapine is a weak inhibitor of CYP2D6. Asenapine does not cause induction of CYP1A2 or CYP3A4 activities in cultured human hepatocytes. Coadministration of asenapine with known inhibitors, inducers or substrates of these metabolic pathways has been studied in a number of drug-drug interaction studies [see Drug Interactions (7.1)].

Food: A crossover study in 26 healthy adult male subjects was performed to evaluate the effect of food on the pharmacokinetics of a single 5 mg dose of asenapine. Consumption of food immediately prior to sublingual administration decreased asenapine exposure by 20%; consumption of food 4 hours after sublingual administration decreased asenapine exposure by about 10%. These effects are probably due to increased hepatic blood flow.

In clinical trials establishing the efficacy and safety of SAPHRIS, patients were instructed to avoid eating for 10 minutes following sublingual dosing. There were no other restrictions with regard to the timing of meals in these trials [see Dosage and Administration (2.1)].

Water: In clinical trials establishing the efficacy and safety of SAPHRIS, patients were instructed to avoid drinking for 10 minutes following sublingual dosing. The effect of water administration following 10 mg sublingual SAPHRIS dosing was studied at different time points of 2, 5, 10, and 30 minutes in 15 healthy adult male subjects. The exposure of asenapine following administration of water 10 minutes after sublingual dosing was equivalent to that when water was administered 30 minutes after dosing. Reduced exposure to asenapine was observed following water administration at 2 minutes (19% decrease) and 5 minutes (10% decrease) [see Dosage and Administration (2.1)].

Drug Interaction Studies:

Effects of other drugs on the exposure of asenapine are summarized in Figure 1. In addition, a population pharmacokinetic analysis indicated that the concomitant administration of lithium had no effect on the pharmacokinetics of asenapine.

Figure 1: Effect of Other Drugs on Asenapine Pharmacokinetics

The effects of asenapine on the pharmacokinetics of other co-administered drugs are summarized in Figure 2. Coadministration of paroxetine with SAPHRIS caused a two-fold increase in the maximum plasma concentrations and systemic exposure of paroxetine. Asenapine enhances the inhibitory effects of paroxetine on its own metabolism by CYP2D6.

Figure 2: Effect of Asenapine on Other Drug Pharmacokinetics

Studies in Special Populations:

Exposures of asenapine in special populations are summarized in Figure 3. Additionally, based on population pharmacokinetic analysis, no effects of sex, race, BMI, and smoking status on asenapine exposure were observed. Exposure in elderly patients is 30-40% higher as compared to adults.

Figure 3: Effect of Intrinsic Factors on Asenapine Pharmacokinetics

13 NONCLINICAL TOXICOLOGY

13.1 Carcinogenesis, Mutagenesis, Impairment of Fertility

Carcinogenesis: In a lifetime carcinogenicity study in CD-1 mice asenapine was administered subcutaneously at doses up to those resulting in plasma levels (AUC) estimated to be 5 times those in humans receiving the MRHD of 10 mg twice daily. The incidence of malignant lymphomas was increased in female mice, with a no-effect dose resulting in plasma levels estimated to be 1.5 times those in humans receiving the MRHD. The mouse strain used has a high and variable incidence of malignant lymphomas, and the significance of these results to humans is unknown. There were no increases in other tumor types in female mice. In male mice, there were no increases in any tumor type.

In a lifetime carcinogenicity study in Sprague-Dawley rats, asenapine did not cause any increases in tumors when administered subcutaneously at doses up to those resulting in plasma levels (AUC) estimated to be 5 times those in humans receiving the MRHD.

Mutagenesis: No evidence for genotoxic potential of asenapine was found in the in vitro bacterial reverse mutation assay, the in vitro forward gene mutation assay in mouse lymphoma cells, the in vitro chromosomal aberration assays in human lymphocytes, the in vitro sister chromatid exchange assay in rabbit lymphocytes, or the in vivo micronucleus assay in rats.

Impairment of Fertility: Asenapine did not impair fertility in rats when tested at doses up to 11 mg/kg twice daily given orally. This dose is 10 times the maximum recommended human dose of 10 mg twice daily given sublingually on a mg/m^2 basis.

14 CLINICAL STUDIES

Efficacy of SAPHRIS was established in the following trials:

- Two fixed-dose, short-term trials and one flexible-dose, maintenance trial in adult patients with schizophrenia as monotherapy [see Clinical Studies (14.1)]
- One fixed-dose and two flexible-dose, short-term trials of monotherapy in adults with manic or mixed episodes associated with bipolar I disorder [see Clinical Studies (14.2)]
- One flexible-dose, maintenance trial of monotherapy in adults with bipolar I disorder [see Clinical Studies (14.2)]
- One fixed-dose, short term trial of monotherapy in children (10 to 17 years) with manic or mixed episodes associated with bipolar I disorder [see Clinical Studies (14.2)]
- One flexible-dose, short-term trial in adult patients with manic or mixed episode associated with bipolar I disorder as adjunctive treatment to lithium or valproate [see Clinical Studies (14.2)]

14.1 Schizophrenia

The efficacy of SAPHRIS in the treatment of schizophrenia in adults was evaluated in three fixed-dose, short-term (6 week), randomized, double-blind, placebo-controlled, and active-controlled (haloperidol, risperidone, and olanzapine) trials of adult patients who met DSM-IV criteria for schizophrenia and were having an acute exacerbation of their schizophrenic illness. In two of the three trials SAPHRIS demonstrated superior efficacy to placebo. In a third trial, SAPHRIS could not be distinguished from placebo; however, an active control in that trial was superior to placebo.

In the two positive trials for SAPHRIS, the primary efficacy rating scale was the Positive and Negative Syndrome Scale (PANSS). The PANSS is a 30 item scale that measures positive symptoms of schizophrenia (7 items), negative symptoms of schizophrenia (7 items), and general psychopathology (16 items), each rated on a scale of 1 (absent) to 7 (extreme); total PANSS scores range from 30 to 210. The primary endpoint was change from baseline to endpoint on the PANSS total score. The results of the SAPHRIS trials in schizophrenia follow:

In trial 1, a 6-week trial (n=174), comparing SAPHRIS (5 mg twice daily) to placebo, SAPHRIS 5 mg twice daily was statistically superior to placebo on the PANSS total score (Trial 1 in Table 13).

In trial 2, a 6-week trial (n=448), comparing two fixed doses of SAPHRIS (5 mg and 10 mg twice daily) to placebo, SAPHRIS 5 mg twice daily was statistically superior to placebo on the PANSS total score. SAPHRIS 10 mg twice daily showed no added benefit compared to 5 mg twice daily and was not significantly different from placebo (Trial 2 in Table 13).

An examination of population subgroups did not reveal any clear evidence of differential responsiveness on the basis of age, sex or race.

Table 13: Short-Term Schizophrenia Trials Establishing Efficacy in Adults
Trial Number | Treatment Group | Primary Efficacy Measure: PANSS Total Score
 |  | Mean Baseline Score (SD) | LS Mean Change from Baseline (SE) | Placebo-subtracted Differencea (95% CI)
Trial 1 | SAPHRIS 5 mg* twice daily | 96.5 (16.4) | -14.4 (2.6) | -9.7 (-17.6, -1.8)
 | Placebo | 92.4 (14.9) | -4.6 (2.5) | --
Trial 2 | SAPHRIS 5 mg* twice daily | 89.2 (12.0) | -16.2 (1.7) | -5.5 (-10.7, -0.2)
 | SAPHRIS 10 mg twice daily | 89.1 (12.9) | -14.9 (1.7) | -4.1 (-9.4, 1.2)
 | Placebo | 88.9 (11.7) | -10.7 (1.6) | --
SD: standard deviation; SE: standard error; LS Mean: least-squares mean; CI: confidence interval, not adjusted for multiple comparisons.
a Difference (drug minus placebo) in least-squares mean change from baseline.
* Doses that are demonstrated to be effective.

Maintenance of efficacy has been demonstrated in a placebo-controlled, double-blind, multicenter, flexible dose (5 mg or 10 mg twice daily based on tolerability) clinical trial with a randomized withdrawal design. All patients were initially administered 5 mg twice daily for 1 week and then titrated up to 10 mg twice daily. A total of 700 patients entered open-label treatment with SAPHRIS for a period of 26 weeks. Of these, a total of 386 patients who met pre-specified criteria for continued stability (mean length of stabilization was 22 weeks) were randomized to a double-blind, placebo-controlled, randomized withdrawal phase. SAPHRIS was statistically superior to placebo in time to relapse or impending relapse defined as increase in PANSS ≥20% from baseline and a Clinical Global Impression–Severity of Illness (CGI-S) score ≥4 (at least 2 days within 1 week) or PANSS score ≥5 on “hostility” or “uncooperativeness” items and CGI-S score ≥4 (≥2 days within a week), or PANSS score ≥5 on any two of the following items: “unusual thought content,” “conceptual disorganization,” or “hallucinatory behavior” items, and CGI-S score ≥4 (≥2 days within 1 week) or investigator judgment of worsening symptoms or increased risk of violence to self (including suicide) or other persons. The Kaplan-Meier curves of the time to relapse or impending relapse during the double-blind, placebo-controlled, randomized withdrawal phase of this trial for SAPHRIS and placebo are shown in Figure 4.

Figure 4: Kaplan-Meier Estimation of Percent Relapse/Impending Relapse for SAPHRIS and placebo

14.2 Bipolar I Disorder

Monotherapy

Adults: The efficacy of SAPHRIS in the treatment of acute mania was established in two similarly designed 3-week, randomized, double-blind, placebo-controlled, and active-controlled (olanzapine) trials of adult patients who met DSM-IV criteria for Bipolar I Disorder with an acute manic or mixed episode with or without psychotic features.

The primary rating instrument used for assessing manic symptoms in these trials was the Young Mania Rating Scale (YMRS), an 11-item clinician-rated scale traditionally used to assess the degree of manic symptomatology in a range from 0 (no manic features) to 60 (maximum score). Patients were also assessed on the Clinical Global Impression – Bipolar (CGI-BP) scale. In both trials, all patients randomized to SAPHRIS were initially administered 10 mg twice daily, and the dose could be adjusted within the dose range of 5 to 10 mg twice daily from Day 2 onward based on efficacy and tolerability. Ninety percent of patients remained on the 10 mg twice daily dose. SAPHRIS was statistically superior to placebo on the YMRS total score and the CGI-BP Severity of Illness score (mania) in both studies (Trials 1 and 2 in Table 14).

In another 3-week, randomized, double-blind, placebo-controlled trial (n=359), comparing two fixed doses of SAPHRIS (5 mg and 10 mg twice daily) to placebo, both doses were statistically superior to placebo on the YMRS total score and CGI-BP Severity of Illness overall score. (Trial 3 in Table 14).

An examination of subgroups did not reveal any clear evidence of differential responsiveness on the basis of age, sex, or race.

Maintenance of efficacy has been demonstrated in a placebo-controlled, double-blind, multicenter, flexible dose (5 mg or 10 mg twice daily based on tolerability) clinical trial with a randomized withdrawal design. All patients were initially administered 5 or 10 mg twice daily, and the option to titrate down to 5 mg twice daily was provided based on tolerability. A total of 549 patients entered open-label treatment with SAPHRIS for a period of 12 to 16 weeks. Of these, a total of 252 patients who met pre-specified criteria for continued stability were randomized to and treated in a double-blind, placebo-controlled, randomized withdrawal phase. SAPHRIS was statistically superior to placebo in time to relapse defined as 1) YMRS or MADRS score ≥ 16; 2) requirement or initiation of any non-study medication to treat mixed, manic, or depressive symptoms, including an antipsychotic, antidepressant, or mood-stabilizing agent; 3) requirement or initiation of psychiatric hospitalization; 4) investigator judgment to discontinue the study due to a mood event. The Kaplan-Meier curves of the time to relapse during the double-blind, placebo-controlled, randomized withdrawal phase of this trial for SAPHRIS and placebo are shown in Figure 5.

Figure 5: Kaplan-Meier Estimation of Percent Relapse for SAPHRIS and Placebo

Time (days) represents the number of days from randomization in the double-blind period to the first date of achieving relapse status.

The product limit estimators are based on the Kaplan-Meier distribution with censoring at last contact date.

Pediatric patients: The efficacy of SAPHRIS in the treatment of acute mania was established in a single, 3-week, placebo-controlled, double-blind trial of 403 pediatric patients 10 to 17 years of age, of whom 302 patients received SAPHRIS at fixed doses of 2.5 mg, 5 mg and 10 mg twice daily. All patients were started on 2.5 mg twice daily. For those assigned to 5 mg twice daily, the dose was increased to 5 mg twice daily after 3 days. For those assigned to 10 mg twice daily, the dose was increased from 2.5 to 5 mg twice daily after 3 days, and then to 10 mg twice daily after 3 additional days.

SAPHRIS was statistically superior to placebo in improving YMRS total score and the CGI-BP Severity of Illness overall score as measured by the change from baseline to week 3 (Trial 3 Pediatric in Table 14). An examination of subgroups did not reveal any clear evidence of differential responsiveness on the basis of age, sex, and race.

Adjunctive Therapy: The efficacy of SAPHRIS as an adjunctive therapy in acute mania was established in a 12-week, placebo-controlled trial with a 3-week primary efficacy endpoint involving 326 adult patients with a manic or mixed episode of Bipolar I Disorder, with or without psychotic features, who were partially responsive to lithium or valproate monotherapy after at least 2 weeks of treatment. All patients randomized to SAPHRIS were initially administered 5 mg twice daily, and the dose could be adjusted within the dose range of 5 to 10 mg twice daily from Day 2 onward based on efficacy and tolerability. SAPHRIS was statistically superior to placebo in the reduction of manic symptoms (measured by the YMRS total score) as an adjunctive therapy to lithium or valproate monotherapy at Week 3 (Trial 5 Adjunctive in Table 14).

Table 14: Acute Bipolar I Trials Establishing Efficacy in Adults and Pediatric Patients 10 to 17 Years
Study Number | Treatment Group | Primary Efficacy Measure: YMRS Total Score
 |  | Mean Baseline Score (SD) | LS Mean Change from Baseline (SE) | Placebo-subtracted Differencea (95% CI)
Trial 1 | SAPHRIS 5-10 mg* twice daily | 29.4 (6.7) | -11.5 (0.8) | -3.7 (-6.6, -0.7)
 | Placebo | 28.3 (6.3) | -7.8 (1.1) | --
Trial 2 | SAPHRIS 5-10 mg* twice daily | 28.3 (5.5) | -10.8 (0.8) | -5.3 (-8.0, -2.5)
 | Placebo | 29.0 (6.1) | -5.5 (1.0) | --
Trial 3 | SAPHRIS 5 mg* twice daily SAPHRIS 10 mg* twice daily Placebo | 29.7 (5.9) 30.2 (5.4) 30.0 (5.6) | -14.4 (1.0) -14.9 (1.0) -10.9 (1.0) | -3.5 (-6.3, -0.7) -4.0 (-6.9, -1.2) --
Trial 4 (Pediatric 10 to 17 years) | SAPHRIS 2.5 mg* twice daily | 29.5 (5.7) | -12.8 (0.8) | -3.2 (-5.6, -0.8)
 | SAPHRIS 5 mg* twice daily | 30.4 (5.9) | -14.9 (0.8) | -5.3 (-7.7, -2.9)
 | SAPHRIS 10 mg* twice daily | 30.1 (5.7) | -15.8 (0.9) | -6.2 (-8.6, -3.8)
 | Placebo | 30.1 (5.7) | - 9.6 (0.9) | --
Trial 5 (Adjunctive) | SAPHRIS 5-10 mg* twice daily + lithium/ Valproate | 28.0 (5.6) | -10.3 (0.8) | -2.4 (-4.4, -0.3)
 | Lithium/Valproate | 28.2 (5.8) | -7.9 (0.8) | --
SD: standard deviation; SE: standard error; LS Mean: least-squares mean; CI: confidence interval, not adjusted for multiple comparisons.
a Difference (drug minus placebo) in least-squares mean change from baseline.
* Doses that are demonstrated to be effective.

16 HOW SUPPLIED/STORAGE AND HANDLING

SAPHRIS (asenapine) sublingual tablets are supplied as:

2.5 mg Tablets, black cherry flavor

Round, white to off-white sublingual tablets, with a hexagon on one side.

Child-resistant packaging

Box of 60 6 blisters with 10 tablets NDC 0456-2402-60

Hospital Unit Dose

Box of 100 10 blisters with 10 tablets NDC 0456-2402-63

5 mg Tablets, black cherry flavor

Round, white to off-white sublingual tablets, with “5” on one side within a circle.

Child-resistant packaging

Box of 60 6 blisters with 10 tablets NDC 0456-2405-60

Hospital Unit Dose

Box of 100 10 blisters with 10 tablets NDC 0456-2405-63

10 mg Tablets, black cherry flavor

Round, white to off-white sublingual tablets, with “10” on one side within a circle.

Child-resistant packaging

Box of 60 6 blisters with 10 tablets NDC 0456-2410-60

Hospital Unit Dose

Box of 100 10 blisters with 10 tablets NDC 0456-2410-63

Storage

Store at 20 º C to 25 º C (68 º F to 77 º F); excursions permitted between 15 º C and 30 º C (59 º F and 86 º F) [see USP Controlled Room Temperature].

17 PATIENT COUNSELING INFORMATION

Advise the patient to read the FDA-approved patient labeling (Instructions for Use).

Dosage and Administration

Counsel patients on proper sublingual administration of SAPHRIS and advise them to read the FDA-approved patient labeling (Instructions for Use). When initiating treatment with SAPHRIS, provide dosage escalation instructions [see Dosage and Administration (2)].

Hypersensitivity Reactions

Counsel patients on the signs and symptoms of a serious allergic reaction (e.g., difficulty breathing, itching, swelling of the face, tongue or throat, feeling lightheaded etc.) and to seek immediate emergency assistance if they develop any of these signs and symptoms [see Contraindications (4), Warnings and Precautions (5.6) and Adverse Reactions (6)].

Application Site Reactions

Inform patients that application site reactions, primarily in the sublingual area, including oral ulcers, blisters, peeling/sloughing and inflammation have been reported. Instruct patients to monitor for these reactions [see Adverse Reactions (6.2)]. Inform patients that numbness or tingling of the mouth or throat may occur directly after administration of SAPHRIS and usually resolves within 1 hour [see Adverse Reactions (6.1)].

Neuroleptic Malignant Syndrome

Counsel patients about a potentially fatal symptom complex sometimes referred to as Neuroleptic Malignant Syndrome (NMS) that has been reported in association with administration of antipsychotic drugs. Patients should contact their health care provider or report to the emergency room if they experience the following signs and symptoms of NMS, including hyperpyrexia, muscle rigidity, altered mental status, and evidence of autonomic instability (irregular pulse or blood pressure, tachycardia, diaphoresis, and cardiac dysrhythmia) [see Warnings and Precautions (5.3)].

Tardive Dyskinesia

Counsel patients on the signs and symptoms of tardive dyskinesia and to contact their health care provider if these abnormal movements occur [see Warnings and Precautions (5.4)].

Metabolic Changes (Hyperglycemia and Diabetes Mellitus, Dyslipidemia, and Weight Gain)

Educate patients about the risk of metabolic changes, how to recognize symptoms of hyperglycemia (high blood sugar) and diabetes mellitus, and the need for specific monitoring, including blood glucose, lipids, and weight [see Warnings and Precautions (5.5)].

Orthostatic Hypotension

Educate patients about the risk of orthostatic hypotension (symptoms include feeling dizzy or lightheaded upon standing) especially early in treatment, and also at times of re-initiating treatment or increases in dose [see Warnings and Precautions (5.7)].

Leukopenia/Neutropenia

Advise patients with a pre-existing low WBC or a history of drug induced leukopenia/neutropenia they should have their CBC monitored while taking SAPHRIS [see Warnings and Precautions (5.9)].

Hyperprolactinemia

Counsel patients on the signs and symptoms of hyperprolactinemia and to contact their health care provider if these abnormalities occur [see Warnings and Precautions (5.11)].

Interference with Cognitive and Motor Performance

Caution patients about performing activities requiring mental alertness, such as operating hazardous machinery or operating a motor vehicle, until they are reasonably certain that SAPHRIS therapy does not affect them adversely [see Warnings and Precautions (5.13)].

Heat Exposure and Dehydration

Counsel patients regarding appropriate care in avoiding overheating and dehydration [see Warnings and Precautions (5.14)].

Concomitant Medications

Advise patients to inform their health care provider if they are taking, or plan to take, any prescription or over-the-counter medications since there is a potential for interactions [see Drug Interactions (7.1)].

Pregnancy

Advise patients that SAPHRIS may cause fetal harm as well as extrapyramidal and/or withdrawal symptoms in a neonate. Advise patients to notify their healthcare provider with a known or suspected pregnancy [see Use in Specific Populations (8.1)].

Pregnancy Registry

Advise patients that there is a pregnancy exposure registry that monitors pregnancy outcomes in women exposed to SAPHRIS during pregnancy [see Use in Specific Populations (8.1)].

Distributed by:
AbbVie Inc.
North Chicago, IL 60064, USA

© 2025 N. V. Organon; used by AbbVie under license.
© 2025 AbbVie. All rights reserved.

The trademarks SAPHRIS, SAPHRIS & Star Design, and Star Design are used by AbbVie under license from N. V. Organon.

20090768

INSTRUCTIONS FOR USE

SAPHRIS® (asenapine)

sublingual tablets

Read these Instructions for Use before you start using SAPHRIS and each time you get a refill. There may be new information. This leaflet does not take the place of talking to your doctor about your medical condition or your treatment.

IMPORTANT:

- For sublingual (under your tongue) use only
- Do not remove tablet until ready to administer.
- Use dry hands when handling tablet.

Your SAPHRIS tablets

Directions for Taking your SAPHRIS Tablets:

Step 1. Firmly press and hold thumb button, then pull out the tablet pack (see Figure A). Do not push tablet through the tablet pack. Do not cut or tear the tablet pack.

Figure A

Step 2. Peel back the colored tab (see Figure B).

Figure B

Step 3. Gently remove the tablet (see Figure C). Do not split, cut or crush the tablet.

Figure C

Step 4. Place the whole tablet under tongue and allow it to dissolve completely (see Figure D).

Figure D

Do not chew or swallow the tablet.

Do not eat or drink for 10 minutes (See Figure E).

Figure E

Step 5. Slide the tablet pack back into case until it clicks (see Figure F).

Figure F

Storing SAPHRIS tablets:

Store SAPHRIS tablets at room temperature between 68°F to 77°F (20°C to 25°C).

These Instructions for Use have been approved by the U.S. Food and Drug Administration.

Distributed by:
AbbVie Inc.
North Chicago, IL 60064, USA

© 2024 N. V. Organon; used by AbbVie under license.
© 2024 AbbVie. All rights reserved.

The trademarks SAPHRIS, SAPHRIS & Star Design, and Star Design are used by AbbVie under license from N. V. Organon.

Revised: June 2024

20090768

PRINCIPAL DISPLAY PANEL

NDC 0456-2402-06
Rx only
10 Tablets
Saphris® 2.5 mg
(asenapine) sublingual tablets
For opening and use instructions, see other side.
Black Cherry Flavor

PRINCIPAL DISPLAY PANEL

Rx only
NDC 0456-2402-60
Saphris® 2.5 mg
(asenapine) sublingual tablets
60 Tablets
Black Cherry
Flavor

PRINCIPAL DISPLAY PANEL

Rx only
Saphris
5 mg
Black Cherry
100 Tablets

PRINCIPAL DISPLAY PANEL

Rx only

NDC 0456-2405-60
Saphris® 5 mg
(asenapine) sublingual tablets
60 Tablets
Black Cherry
Flavor

PRINCIPAL DISPLAY PANEL

Rx only
NDC 0456-2410-60
Saphris® 10 mg
(asenapine) sublingual tablets
60 Tablets
Black Cherry
Flavor

PRINCIPAL DISPLAY PANEL

Rx only
NDC 0456-2410-63
Saphris® 10 mg
(asenapine) sublingual tablets
Black Cherry
Flavor
100 Tablets
HOSPITAL UNIT DOSE